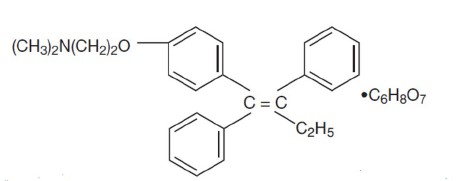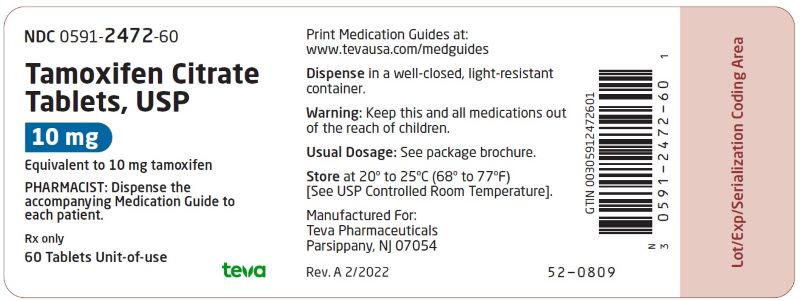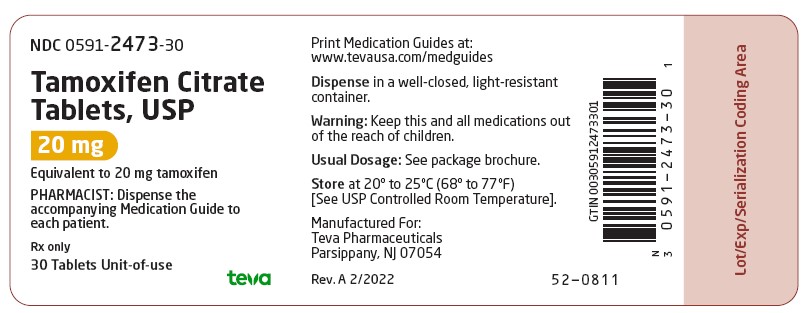 DRUG LABEL: Tamoxifen Citrate
NDC: 0591-2472 | Form: TABLET
Manufacturer: Actavis Pharma, Inc.
Category: prescription | Type: HUMAN PRESCRIPTION DRUG LABEL
Date: 20251218

ACTIVE INGREDIENTS: TAMOXIFEN CITRATE 10 mg/1 1
INACTIVE INGREDIENTS: CROSCARMELLOSE SODIUM; LACTOSE MONOHYDRATE; MAGNESIUM STEARATE; CELLULOSE, MICROCRYSTALLINE; STARCH, CORN

Tamoxifen Citrate Tablets, USP
Rx only

WARNING

For Women with Ductal Carcinoma in Situ (DCIS) and Women at High Risk for Breast Cancer

Serious and life-threatening events associated with tamoxifen in the risk reduction setting (women at high risk for cancer and women with DCIS) include uterine malignancies, stroke and pulmonary embolism. Incidence rates for these events were estimated from the NSABP P-1 trial (see CLINICAL PHARMACOLOGY, Clinical Studies, Reduction in Breast Cancer Incidence in High Risk Women). Uterine malignancies consist of both endometrial adenocarcinoma (incidence rate per 1,000 women-years of 2.20 for tamoxifen vs. 0.71 for placebo) and uterine sarcoma (incidence rate per 1,000 women-years of 0.17 for tamoxifen vs. 0.4 for placebo)*. For stroke, the incidence rate per 1,000 women-years was 1.43 for tamoxifen vs. 1.00 for placebo**. For pulmonary embolism, the incidence rate per 1,000 women-years was 0.75 for tamoxifen versus 0.25 for placebo**.

Some of the strokes, pulmonary emboli, and uterine malignancies were fatal.

Health care providers should discuss the potential benefits versus the potential risks of these serious events with women at high risk of breast cancer and women with DCIS considering tamoxifen to reduce their risk of developing breast cancer.

The benefits of tamoxifen citrate outweigh its risks in women already diagnosed with breast cancer.

*Updated long-term follow-up data (median length of follow-up is 6.9 years) from NSABP P-1 study. See WARNINGS: Effects on the Uterus-Endometrial Cancer and Uterine Sarcoma.

**See Table 3 under CLINICAL PHARMACOLOGY, Clinical Studies.

DESCRIPTION

Tamoxifen citrate tablets, USP, a nonsteroidal antiestrogen, are for oral administration. Chemically, tamoxifen is the trans-isomer of a triphenylethylene derivative. The chemical name is (Z)2-[4-(1,2-diphenyl-1-butenyl) phenoxy]-N, N-dimethylethanamine 2 hydroxy-1,2,3- propanetricarboxylate (1:1). The structural formula is as follows:

C26H29NO•C6H8O7 Molecular Weight: 563.62

The pKa' is 8.85, the equilibrium solubility in water at 37°C is 0.5 mg/mL and in 0.02 N HCl at 37°C, it is 0.2 mg/mL.

10 mg Tablets: Each tablet contains 15.2 mg of tamoxifen citrate, USP which is equivalent to 10 mg of tamoxifen.

20 mg Tablets: Each tablet contains 30.4 mg of tamoxifen citrate, USP which is equivalent to 20 mg of tamoxifen.

Each tablet contains the following inactive ingredients: croscarmellose sodium, lactose monohydrate, magnesium stearate, microcrystalline cellulose, and pregelatinized maize starch.

CLINICAL PHARMACOLOGY

Tamoxifen citrate is a nonsteroidal agent that has demonstrated potent antiestrogenic properties in animal test systems. The antiestrogenic effects may be related to its ability to compete with estrogen for binding sites in target tissues such as breast. Tamoxifen inhibits the induction of rat mammary carcinoma induced by dimethylbenzanthracene (DMBA) and causes the regression of already established DMBA-induced tumors. In this rat model, tamoxifen appears to exert its antitumor effects by binding the estrogen receptors.

In cytosols derived from human breast adenocarcinomas, tamoxifen competes with estradiol for estrogen receptor protein.

Absorption and Distribution:

Following a single oral dose of 20 mg tamoxifen, an average peak plasma concentration of 40 ng/mL (range 35 to 45 ng/mL) occurred approximately 5 hours after dosing. The decline in plasma concentrations of tamoxifen is biphasic with a terminal elimination half-life of about 5 to 7 days. The average peak plasma concentration of N-desmethyl tamoxifen is 15 ng/mL (range 10 to 20 ng/mL). Chronic administration of 10 mg tamoxifen given twice daily for 3 months to patients results in average steady-state plasma concentrations of 120 ng/mL (range 67 to 183 ng/mL) for tamoxifen and 336 ng/mL (range 148 to 654 ng/mL) for N-desmethyl tamoxifen. The average steady-state plasma concentrations of tamoxifen and N-desmethyl tamoxifen after administration of 20 mg tamoxifen once daily for 3 months are 122 ng/mL (range 71 to 183 ng/mL) and 353 ng/mL (range 152 to 706 ng/mL), respectively. After initiation of therapy, steady-state concentrations for tamoxifen are achieved in about 4 weeks and steady-state concentrations for N-desmethyl tamoxifen are achieved in about 8 weeks, suggesting a half-life of approximately 14 days for this metabolite. In a steady-state, crossover study of 10 mg tamoxifen citrate tablets given twice a day vs. a 20 mg tamoxifen tablet given once daily, the 20 mg tamoxifen citrate tablet was bioequivalent to the 10 mg tamoxifen citrate tablets.

Metabolism:

Tamoxifen is extensively metabolized after oral administration. N-desmethyl tamoxifen is the major metabolite found in patients’ plasma. The biological activity of N-desmethyl tamoxifen appears to be similar to that of tamoxifen. 4-Hydroxytamoxifen and a side chain primary alcohol derivative of tamoxifen have been identified as minor metabolites in plasma. Tamoxifen is a substrate of cytochrome P-450 3A, 2C9 and 2D6, and an inhibitor of P-glycoprotein.

Excretion:

Studies in women receiving 20 mg of ^14C tamoxifen have shown that approximately 65% of the administered dose was excreted from the body over a period of 2 weeks with fecal excretion as the primary route of elimination. The drug is excreted mainly as polar conjugates, with unchanged drug and unconjugated metabolites accounting for less than 30% of the total fecal radioactivity.

Special Populations:

The effects of age, gender and race on the pharmacokinetics of tamoxifen have not been determined. The effects of reduced liver function on the metabolism and pharmacokinetics of tamoxifen have not been determined.

Pediatric Patients

The pharmacokinetics of tamoxifen and N-desmethyl tamoxifen were characterized using a population pharmacokinetic analysis with sparse samples per patient obtained from 27 female pediatric patients aged 2 to 10 years enrolled in a study designed to evaluate the safety, efficacy, and pharmacokinetics of tamoxifen in treating McCune-Albright Syndrome. Rich data from two tamoxifen citrate pharmacokinetic trials in which 59 postmenopausal women with breast cancer completed the studies were included in the analysis to determine the structural pharmacokinetic model for tamoxifen. A one-compartment model provided the best fit to the data.

In pediatric patients, an average steady-state peak plasma concentration (Css, max) and AUC were of 187 ng/mL and 4110 ng hr/mL, respectively, and Css, max occurred approximately 8 hours after dosing. Clearance (CL/F) as body weight adjusted in female pediatric patients was approximately 2.3-fold higher than in female breast cancer patients. In the youngest cohort of female pediatric patients (2 to 6 year olds), CL/F was 2.6-fold higher; in the oldest cohort (7 to 10.9 year olds) CL/F was approximately 1.9-fold higher. Exposure to N-desmethyl tamoxifen was comparable between the pediatric and adult patients. The safety and efficacy of tamoxifen for girls aged 2 to 10 years with McCune-Albright Syndrome and precocious puberty have not been studied beyond one year of treatment. The long-term effects of tamoxifen therapy in girls have not been established. In adults treated with tamoxifen an increase in incidence of uterine malignancies, stroke and pulmonary embolism has been noted (see BOXED WARNING).

Drug-Drug Interactions:

In vitro studies showed that erythromycin, cyclosporin, nifedipine and diltiazem competitively inhibited formation of N-desmethyl tamoxifen with apparent K1 of 20, 1, 45 and 30 µM, respectively. The clinical significance of these in vitro studies is unknown.

Tamoxifen reduced the plasma concentration of letrozole by 37% when these drugs were coadministered. Rifampin, a cytochrome P-450 3A4 inducer reduced tamoxifen AUC and Cmax by 86% and 55%, respectively. Aminoglutethimide reduces tamoxifen and N-desmethyl tamoxifen plasma concentrations. Medroxyprogesterone reduces plasma concentrations of N-desmethyl, but not tamoxifen.

In the anastrozole adjuvant trial, coadministration of anastrozole and tamoxifen citrate in breast cancer patients reduced anastrozole plasma concentration by 27% compared to those achieved with anastrozole alone; however, the coadministration did not affect the pharmacokinetics of tamoxifen or N-desmethyltamoxifen (see PRECAUTIONS-Drug Interactions). Tamoxifen citrate should not be coadministered with anastrozole.

Clinical Studies

Metastatic Breast Cancer:

Premenopausal Women (Tamoxifen vs. Ablation): Three prospective, randomized studies (Ingle, Pritchard, Buchanan) compared tamoxifen to ovarian ablation (oophorectomy or ovarian irradiation) in premenopausal women with advanced breast cancer. Although the objective response rate, time to treatment failure, and survival were similar with both treatments, the limited patient accrual prevented a demonstration of equivalence. In an overview analysis of survival data from the 3 studies, the hazard ratio for death (tamoxifen/ovarian ablation) was 1.00 with two-sided 95% confidence intervals of 0.73 to 1.37. Elevated serum and plasma estrogens have been observed in premenopausal women receiving tamoxifen, but the data from the randomized studies do not suggest an adverse effect of this increase. A limited number of premenopausal patients with disease progression during tamoxifen therapy responded to subsequent ovarian ablation.

Male Breast Cancer: Published results from 122 patients (119 evaluable) and case reports in 16 patients (13 evaluable) treated with tamoxifen citrate have shown that tamoxifen is effective for the palliative treatment of male breast cancer. Sixty-six of these 132 evaluable patients responded to tamoxifen which constitutes a 50% objective response rate.

Adjuvant Breast Cancer:

Overview: The Early Breast Cancer Trialists' Collaborative Group (EBCTCG) conducted worldwide overviews of systemic adjuvant therapy for early breast cancer in 1985, 1990, and again in 1995. In 1998, 10-year outcome data were reported for 36,689 women in 55 randomized trials of adjuvant tamoxifen using doses of 20 to 40 mg/day for 1 to 5+ years. Twenty-five percent of patients received 1 year or less of trial treatment, 52% received 2 years, and 23% received about 5 years. Forty-eight percent of tumors were estrogen receptor (ER) positive (>10 fmol/mg), 21% were ER poor (<10 fmol/l), and 31% were ER unknown. Among 29,441 patients with ER positive or unknown breast cancer, 58% were entered into trials comparing tamoxifen to no adjuvant therapy and 42% were entered into trials comparing tamoxifen in combination with chemotherapy vs. the same chemotherapy alone. Among these patients, 54% had node positive disease and 46% had node negative disease.

Among women with ER positive or unknown breast cancer and positive nodes who received about 5 years of treatment, overall survival at 10 years was 61.4% for tamoxifen vs. 50.5% for control (logrank 2p <0.00001). The recurrence-free rate at 10 years was 59.7% for tamoxifen vs. 44.5% for control (logrank 2p <0.00001). Among women with ER positive or unknown breast cancer and negative nodes who received about 5 years of treatment, overall survival at 10 years was 78.9% for tamoxifen vs. 73.3% for control (logrank 2p <0.00001). The recurrence-free rate at 10 years was 79.2% for tamoxifen vs. 64.3% for control (logrank 2p <0.00001).

The effect of the scheduled duration of tamoxifen may be described as follows. In women with ER positive or unknown breast cancer receiving 1 year or less, 2 years or about 5 years of tamoxifen, the proportional reductions in mortality were 12%, 17%, and 26%, respectively (trend significant at 2p <0.003). The corresponding reductions in breast cancer recurrence were 21%, 29% and 47% (trend significant at 2p <0.00001).

Benefit is less clear for women with ER poor breast cancer in whom the proportional reduction in recurrence was 10% (2p = 0.007) for all durations taken together, or 9% (2p = 0.02) if contralateral breast cancers are excluded. The corresponding reduction in mortality was 6% (NS). The effects of about 5 years of tamoxifen on recurrence and mortality were similar regardless of age and concurrent chemotherapy. There was no indication that doses greater than 20 mg per day were more effective.

Anastrozole Adjuvant ATAC Trial - Study of Anastrozole compared to Tamoxifen for Adjuvant Treatment of Early Breast Cancer: An anastrozole adjuvant trial was conducted in 9366 postmenopausal women with operable breast cancer who were randomized to receive adjuvant treatment with either anastrozole 1 mg daily, tamoxifen citrate 20 mg daily, or a combination of these two treatments for 5 years or until recurrence of the disease. At a median follow-up of 33 months, the combination of anastrozole and tamoxifen citrate did not demonstrate any efficacy benefit when compared with tamoxifen citrate therapy alone in all patients as well as in the hormone receptor-positive subpopulation. This treatment arm was discontinued from the trial. Please refer to CLINICAL PHARMACOLOGY, Special Populations and Drug-Drug Interactions, PRECAUTIONS, Laboratory Tests, PRECAUTIONS, Drug Interactions and ADVERSE REACTIONS for safety information from this trial. Please refer to the full prescribing information for ARIMIDEX® (anastrozole) 1 mg tablets for additional information on this trial.

Patients in the two monotherapy arms of the ATAC trial were treated for a median of 60 months (5 years) and followed for a median of 68 months. Disease-free survival in the intent-to-treat population was statistically significantly improved [Hazard Ratio (HR) = 0.87, 95% CI: 0.78, 0.97, p=0.0127] in the anastrozole arm compared to the tamoxifen citrate arm.

Node Positive-Individual Studies: Two studies (Hubay and NSABP B-09) demonstrated an improved disease-free survival following radical or modified radical mastectomy in postmenopausal women or women 50 years of age or older with surgically curable breast cancer with positive axillary nodes when tamoxifen was added to adjuvant cytotoxic chemotherapy. In the Hubay study, tamoxifen citrate was added to "low-dose" CMF (cyclophosphamide, methotrexate and fluorouracil). In the NSABP B-09 study, tamoxifen was added to melphalan [L-phenylalanine mustard (P)] and fluorouracil (F).

In the Hubay study, patients with a positive (more than 3 fmol) estrogen receptor were more likely to benefit. In the NSABP B-09 study in women age 50 to 59 years, only women with both estrogen and progesterone receptor levels 10 fmol or greater clearly benefited, while there was a nonstatistically significant trend toward adverse effect in women with both estrogen and progesterone receptor levels less than 10 fmol. In women age 60 to 70 years, there was a trend toward a beneficial effect of tamoxifen citrate without any clear relationship to estrogen or progesterone receptor status.

Three prospective studies (ECOG-1178, Toronto, NATO) using tamoxifen adjuvantly as a single agent demonstrated an improved disease-free survival following total mastectomy and axillary dissection for postmenopausal women with positive axillary nodes compared to placebo/no treatment controls. The NATO study also demonstrated an overall survival benefit.

Node Negative-Individual Studies: NSABP B-14, a prospective, double-blind, randomized study, compared tamoxifen to placebo in women with axillary node-negative, estrogen-receptor positive (≥10 fmol/mg cytosol protein) breast cancer (as adjuvant therapy, following total mastectomy and axillary dissection, or segmental resection, axillary dissection, and breast radiation). After five years of treatment, there was a significant improvement in disease-free survival in women receiving tamoxifen. This benefit was apparent both in women under age 50 and in women at or beyond age 50.

One additional randomized study (NATO) demonstrated improved disease-free survival for tamoxifen compared to no adjuvant therapy following total mastectomy and axillary dissection in postmenopausal women with axillary node-negative breast cancer. In this study, the benefits of tamoxifen appeared to be independent of estrogen receptor status.

Duration of Therapy: In the EBCTCG 1995 overview, the reduction in recurrence and mortality was greater in those studies that used tamoxifen for about 5 years than in those that used tamoxifen for a shorter period of therapy.

In the NSABP B-14 trial, in which patients were randomized to tamoxifen 20 mg/day for 5 years vs. placebo and were disease-free at the end of this 5-year period were offered rerandomization to an additional 5 years of tamoxifen or placebo. With 4 years of follow-up after this rerandomization, 92% of the women that received 5 years of tamoxifen were alive and disease-free, compared to 86% of the women scheduled to receive 10 years of tamoxifen (p=0.003). Overall survivals were 96% and 94%, respectively (p=0.08). Results of the B-14 study suggest that continuation of therapy beyond 5 years does not provide additional benefit.

A Scottish trial of 5 years of tamoxifen vs. indefinite treatment found a disease-free survival of 70% in the five-year group and 61% in the indefinite group, with 6.2 years median follow-up (HR=1.27, 95% CI: 0.87 to 1.85).

In a large randomized trial conducted by the Swedish Breast Cancer Cooperative Group of adjuvant tamoxifen 40 mg/day for 2 or 5 years, overall survival at 10 years was estimated to be 80% in the patients in the 5-year tamoxifen group, compared with 74% among corresponding patients in the 2-year treatment group (p=0.03). Disease-free survival at 10 years was 73% in the 5-year group and 67% in the 2-year group (p=0.009). Compared with 2 years of tamoxifen treatment, 5 years of treatment resulted in a slightly greater reduction in the incidence of contralateral breast cancer at 10 years, but this difference was not statistically significant.

Contralateral Breast Cancer: The incidence of contralateral breast cancer is reduced in breast cancer patients (premenopausal and postmenopausal) receiving tamoxifen compared to placebo. Data on contralateral breast cancer are available from 32,422 out of 36,689 patients in the 1995 overview analysis of the Early Breast Cancer Trialists Collaborative Group (EBCTCG). In clinical trials with tamoxifen of 1 year or less, 2 years, and about 5 years duration, the proportional reductions in the incidence rate of contralateral breast cancer among women receiving tamoxifen were 13% (NS), 26% (2p = 0.004) and 47% (2p <0.00001), with a significant trend favoring longer tamoxifen duration (2p = 0.008). The proportional reductions in the incidence of contralateral breast cancer were independent of age and ER status of the primary tumor. Treatment with about 5 years of tamoxifen citrate reduced the annual incidence rate of contralateral breast cancer from 7.6 per 1,000 patients in the control group compared with 3.9 per 1,000 patients in the tamoxifen group.

In a large randomized trial in Sweden (the Stockholm Trial) of adjuvant tamoxifen 40 mg/day for 2 to 5 years, the incidence of second primary breast tumors was reduced 40% (p <0.008) on tamoxifen compared to control. In the NSABP B-14 trial in which patients were randomized to tamoxifen 20 mg/day for 5 years vs. placebo, the incidence of second primary breast cancers was also significantly reduced (p <0.01). In NSABP B-14, the annual rate of contralateral breast cancer was 8.0 per 1,000 patients in the placebo group compared with 5.0 per 1,000 patients in the tamoxifen group, at 10 years after first randomization.

Ductal Carcinoma in Situ:

NSABP B-24, a double-blind, randomized trial included women with ductal carcinoma in situ (DCIS). This trial compared the addition of tamoxifen or placebo to treatment with lumpectomy and radiation therapy for women with DCIS. The primary objective was to determine whether 5 years of tamoxifen therapy (20 mg/day) would reduce the incidence of invasive breast cancer in the ipsilateral (the same) or contralateral (the opposite) breast.

In this trial 1,804 women were randomized to receive either tamoxifen or placebo for 5 years: 902 women were randomized to tamoxifen 10 mg tablets twice a day and 902 women were randomized to placebo. As of December 31, 1998, follow-up data were available for 1,798 women and the median duration of follow-up was 74 months.

The tamoxifen and placebo groups were well balanced for baseline demographic and prognostic factors. Over 80% of the tumors were less than or equal to 1 cm in their maximum dimension, were not palpable, and were detected by mammography alone. Over 60% of the study population was postmenopausal. In 16% of patients, the margin of the resected specimen was reported as being positive after surgery. Approximately half of the tumors were reported to contain comedo necrosis.

For the primary endpoint, the incidence of invasive breast cancer was reduced by 43% among women assigned to tamoxifen (44 cases-tamoxifen, 74 cases-placebo; p=0.004; relative risk (RR)=0.57, 95% CI: 0.39 to 0.84). No data are available regarding the ER status of the invasive cancers. The stage distribution of the invasive cancers at diagnosis was similar to that reported annually in the SEER data base.

Results are shown in Table 1. For each endpoint the following results are presented: the number of events and rate per 1,000 women per year for the placebo and tamoxifen groups; and the relative risk (RR) and its associated 95% confidence interval (CI) between tamoxifen and placebo. Relative risks less than 1.0 indicate a benefit of tamoxifen citrate therapy. The limits of the confidence intervals can be used to assess the statistical significance of the benefits of tamoxifen therapy. If the upper limit of the CI is less than 1.0, then a statistically significant benefit exists.

Table 1: Major Outcomes of the NSABP B-24 Trial
Type of Event | Lumpectomy, radiotherapy, and placebo |  | Lumpectomy, radiotherapy, and tamoxifen |  | RR | 95% CI Limits
Type of Event | No. of events | Rate per 1,000 women per year | No. of events | Rate per 1,000 women per year
Invasive Breast Cancer (Primary Endpoint) | 74 | 16.73 | 44 | 9.60 | 0.57 | 0.39 to 0.84
Ipsilateral | 47 | 10.61 | 27 | 5.90 | 0.56 | 0.33 to 0.91
Contralateral | 25 | 5.64 | 17 | 3.71 | 0.66 | 0.33 to 1.27
Side undetermined | 2 | - | 0 | - | -
Secondary Endpoints
DCIS | 56 | 12.66 | 41 | 8.95 | 0.71 | 0.46 to 1.08
Ipsilateral | 46 | 10.40 | 38 | 8.29 | 0.88 | 0.51 to 1.25
Contralateral | 10 | 2.26 | 3 | 0.65 | 0.29 | 0.05 to 1.13
All Breast Cancer Events | 129 | 29.16 | 84 | 18.34 | 0.63 | 0.47 to 0.83
All ipsilateral events | 96 | 21.70 | 65 | 14.19 | 0.65 | 0.47 to 0.91
All contralateral events | 37 | 8.36 | 20 | 4.37 | 0.52 | 0.29 to 0.92
Deaths | 32 |  | 28
Uterine Malignancies^1 | 4 |  | 9
Endometrial Adenocarcinoma^1 | 4 | 0.57 | 8 | 1.15
Uterine Sarcoma^1 | 0 | 0.0 | 1 | 0.14
Second primary malignancies (other than endometrial and breast) | 30 |  | 29
Stroke | 2 |  | 7
Thromboembolic events (DVT, PE) | 5 |  | 15
^1Updated follow-up data (median 8.1 years)

Survival was similar in the placebo and tamoxifen groups. At 5 years from study entry, survival was 97% for both groups.

Reduction in Breast Cancer Incidence in High Risk Women:

The Breast Cancer Prevention Trial (BCPT, NSABP P-1) was a double-blind, randomized, placebo-controlled trial with a primary objective to determine whether 5 years of tamoxifen citrate therapy (20 mg/day) would reduce the incidence of invasive breast cancer in women at high risk for the disease (see INDICATIONS AND USAGE). Secondary objectives included an evaluation of the incidence of ischemic heart disease; the effects on the incidence of bone fractures; and other events that might be associated with the use of tamoxifen, including: endometrial cancer, pulmonary embolus, deep-vein thrombosis, stroke, and cataract formation and surgery (see WARNINGS).

The Gail Model was used to calculate predicted breast cancer risk for women who were less than 60 years of age and did not have lobular carcinoma in situ (LCIS). The following risk factors were used: age; number of first-degree female relatives with breast cancer; previous breast biopsies; presence or absence of atypical hyperplasia; nulliparity; age at first live birth; and age at menarche. A 5-year predicted risk of breast cancer of ≥1.67% was required for entry into the trial.

In this trial, 13,388 women of at least 35 years of age were randomized to receive either tamoxifen or placebo for five years. The median duration of treatment was 3.5 years. As of January 31, 1998, follow-up data is available for 13,114 women. Twenty-seven percent of women randomized to placebo (1,782) and 24% of women randomized to tamoxifen citrate (1,596) completed 5 years of therapy. The demographic characteristics of women on the trial with follow-up data are shown in Table 2.

Table 2: Demographic Characteristics of Women in the NSABP P-1 Trial
Characteristic | Placebo |  | Tamoxifen
 | # | % | # | %
Age (yrs.)
35 to 39 | 184 | 3 | 158 | 2
40 to 49 | 2,394 | 36 | 2,411 | 37
50 to 59 | 2,011 | 31 | 2,019 | 31
60 to 69 | 1,588 | 24 | 1,563 | 24
≥70 | 393 | 6 | 393 | 6
Age at first live birth (yrs.)
Nulliparous | 1,202 | 18 | 1,205 | 18
12 to 19 | 915 | 14 | 946 | 15
20 to 24 | 2,448 | 37 | 2,449 | 37
25 to 29 | 1,399 | 21 | 1,367 | 21
≥30 | 606 | 9 | 577 | 9
Race
White | 6,333 | 96 | 6,323 | 96
Black | 109 | 2 | 103 | 2
Other | 128 | 2 | 118 | 2
Age at menarche
≥14 | 1,243 | 19 | 1,170 | 18
12 to 13 | 3,610 | 55 | 3,610 | 55
≤11 | 1,717 | 26 | 1,764 | 27
# of first degree relatives with breast cancer
0 | 1,584 | 24 | 1,525 | 23
1 | 3,714 | 57 | 3,744 | 57
2+ | 1,272 | 19 | 1,275 | 20
Prior Hysterectomy
No | 4,173 | 63.5 | 4,018 | 62.4
Yes | 2,397 | 36.5 | 2,464 | 37.7
# of previous breast biopsies
0 | 2,935 | 45 | 2,923 | 45
1 | 1,833 | 28 | 1,850 | 28
≥2 | 1,802 | 27 | 1,771 | 27
History of atypical hyperplasia in the breast
No | 5,958 | 91 | 5,969 | 91
Yes | 612 | 9 | 575 | 9
History of LCIS at entry
No | 6,165 | 94 | 6,135 | 94
Yes | 405 | 6 | 409 | 6
5-year predicted breast cancer risk (%)
≤2.00 | 1,646 | 25 | 1,626 | 25
2.01 to 3.00 | 2,028 | 31 | 2,057 | 31
3.01 to 5.00 | 1,787 | 27 | 1,707 | 26
≥5.01 | 1,109 | 17 | 1,162 | 18
Total | 6,570 | 100.0 | 6,544 | 100.0

Results are shown in Table 3. After a median follow-up of 4.2 years, the incidence of invasive breast cancer was reduced by 44% among women assigned to tamoxifen (86 cases-tamoxifen, 156 cases-placebo; p <0.00001; relative risk (RR)=0.56, 95% CI: 0.43 to 0.72). A reduction in the incidence of breast cancer was seen in each prospectively specified age group (≤49, 50 to 59, ≥60), in women with or without LCIS, and in each of the absolute risk levels specified in Table 3. A non-significant decrease in the incidence of ductal carcinoma in situ (DCIS) was seen (23-tamoxifen, 35-placebo; RR=0.66; 95% CI: 0.39 to 1.11).

There was no statistically significant difference in the number of myocardial infarctions, severe angina, or acute ischemic cardiac events between the two groups (61-tamoxifen citrate, 59- placebo; RR=1.04, 95% CI: 0.73 to 1.49).

No overall difference in mortality (53 deaths in tamoxifen group vs. 65 deaths in placebo group) was present. No difference in breast cancer-related mortality was observed (4 deaths in tamoxifen group vs. 5 deaths in placebo group).

Although there was a non-significant reduction in the number of hip fractures (9 on tamoxifen, 20 on placebo) in the tamoxifen group, the number of wrist fractures was similar in the two treatment groups (69 on tamoxifen, 74 on placebo). A subgroup analysis of the P-1 trial, suggests a difference in effect in bone mineral density (BMD) related to menopausal status in patients receiving tamoxifen. In postmenopausal women there was no evidence of bone loss of the lumbar spine and hip. Conversely, tamoxifen citrate was associated with significant bone loss of the lumbar spine and hip in premenopausal women.

The risks of tamoxifen therapy include endometrial cancer, DVT, PE, stroke, cataract formation, and cataract surgery (See Table 3). In the NSABP P-1 trial, 33 cases of endometrial cancer were observed in the tamoxifen group vs. 14 in the placebo group (RR=2.48, 95% CI: 1.27 to 4.92). Deep-vein thrombosis was observed in 30 women receiving tamoxifen vs. 19 in women receiving placebo (RR=1.59, 95% CI: 0.86 to 2.98). Eighteen cases of pulmonary embolism were observed in the tamoxifen group vs. 6 in the placebo group (RR=3.01, 95% CI: 1.15 to 9.27). There were 34 strokes on the tamoxifen arm and 24 on the placebo arm (RR=1.42; 95% CI: 0.82 to 2.51). Cataract formation in women without cataracts at baseline was observed in 540 women taking tamoxifen vs. 483 women receiving placebo (RR=1.13, 95% CI: 1.00 to 1.28). Cataract surgery (with or without cataracts at baseline) was performed in 201 women taking tamoxifen vs. 129 women receiving placebo (RR=1.51, 95% CI: 1.21 to 1.89) (see WARNINGS).

Table 3 summarizes the major outcomes of the NSABP P-1 trial. For each endpoint, the following results are presented: the number of events and rate per 1,000 women per year for the placebo and tamoxifen groups; and the relative risk (RR) and its associated 95% confidence interval (CI) between tamoxifen and placebo. Relative risks less than 1.0 indicate a benefit of tamoxifen therapy. The limits of the confidence intervals can be used to assess the statistical significance of the benefits or risks of tamoxifen therapy. If the upper limit of the CI is less than 1.0, then a statistically significant benefit exists.

For most participants, multiple risk factors would have been required for eligibility. This table considers risk factors individually, regardless of other co-existing risk factors, for women who developed breast cancer. The 5-year predicted absolute breast cancer risk accounts for multiple risk factors in an individual and should provide the best estimate of individual benefit (see INDICATIONS AND USAGE).

Table 3: Major Outcomes of the NSABP P-1 Trial
 | # Of Events |  | Rate/1,000 Women/Year |  | RR | 95% CI; LIMITS
Type of Event | Placebo | Tamoxifen | Placebo | Tamoxifen | RR | 95% CI; LIMITS
Invasive Breast Cancer | 156 | 86 | 6.49 | 3.58 | 0.56 | 0.43 to 0.72
Age ≤49 | 59 | 38 | 6.34 | 4.11 | 0.65 | 0.43 to 0.98
Age 50 to 59 | 46 | 25 | 6.31 | 3.53 | 0.56 | 0.35 to 0.91
Age ≥60 | 51 | 23 | 7.17 | 3.22 | 0.45 | 0.27 to 0.74
Risk Factors for Breast Cancer History, LCIS
No | 140 | 78 | 6.23 | 3.51 | 0.56 | 0.43 to 0.74
Yes | 16 | 8 | 12.73 | 6.33 | 0.50 | 0.21 to 1.17
History, Atypical Hyperplasia
No | 138 | 84 | 6.37 | 3.89 | 0.61 | 0.47 to 0.80
Yes | 18 | 2 | 8.69 | 1.05 | 0.12 | 0.03 to 0.52
No. First Degree Relatives
0 | 32 | 17 | 5.97 | 3.26 | 0.55 | 0.30 to 0.98
1 | 80 | 45 | 5.81 | 3.31 | 0.57 | 0.40 to 0.82
2 | 35 | 18 | 8.92 | 4.67 | 0.52 | 0.30 to 0.92
≥3 | 9 | 6 | 13.33 | 7.58 | 0.57 | 0.20 to 1.59
5-Year Predicted Breast Cancer Risk (as calculated by the Gail Model)
≤2.00% | 31 | 13 | 5.36 | 2.26 | 0.42 | 0.22 to 0.81
2.01 to 3.00% | 39 | 28 | 5.25 | 3.83 | 0.73 | 0.45 to 1.18
3.01 to 5.00% | 36 | 26 | 5.37 | 4.06 | 0.76 | 0.46 to 1.26
≥5.00% | 50 | 19 | 13.15 | 4.71 | 0.36 | 0.21 to 0.61
DCIS | 35 | 23 | 1.47 | 0.97 | 0.66 | 0.39 to 1.11
Fractures (protocol-specified sites) | 92^1 | 76^1 | 3.87 | 3.20 | 0.61 | 0.83 to 1.12
Hip | 20 | 9 | 0.84 | 0.38 | 0.45 | 0.18 to 1.04
Wrist^2 | 74 | 69 | 3.11 | 2.91 | 0.93 | 0.67 to 1.29
Total Ischemic Events | 59 | 61 | 2.47 | 2.57 | 1.04 | 0.71 to 1.51
Myocardial Infarction | 27 | 27 | 1.13 | 1.13 | 1.00 | 0.57 to 1.78
Fatal | 8 | 7 | 0.33 | 0.29 | 0.88 | 0.27 to 2.77
Nonfatal | 19 | 20 | 0.79 | 0.84 | 1.06 | 0.54 to 2.09
Angina^3 | 12 | 12 | 0.50 | 0.50 | 1.00 | 0.41 to 2.44
Acute Ischemic Syndrome^4 | 20 | 22 | 0.84 | 0.92 | 1.11 | 0.58 to 2.13
Uterine
Malignancies (among women with an intact uterus)^10 | 17 | 57
Endometrial Adenocarcinoma^10 | 17 | 53 | 0.71 | 2.20
Uterine Sarcoma^10 | 0 | 4 | 0.0 | 0.17
Stroke^5 | 24 | 34 | 1.00 | 1.43 | 1.42 | 0.82 to 2.51
Transient Ischemic Attack | 21 | 18 | 0.88 | 0.75 | 0.86 | 0.43 to 1.70
Pulmonary Emboli^6 | 6 | 18 | 0.25 | 0.75 | 3.01 | 1.15 to 9.27
Deep-Vein Thrombosis^7 | 19 | 30 | 0.79 | 1.26 | 1.59 | 0.86 to 2.98
Cataracts Developing on Study^8 | 483 | 540 | 22.51 | 25.41 | 1.13 | 1.00 to 1.28
Underwent Cataract Surgery^8 | 63 | 101 | 2.83 | 4.57 | 1.62 | 1.18 to 2.22
Underwent Cataract Surgery^9 | 129 | 201 | 5.44 | 8.56 | 1.58 | 1.26 to 1.97
^1 Two women had hip and wrist fractures
^2 Includes Colles' and other lower radius fractures
^3 Requiring angioplasty or CABG
^4 New Q-wave on ECG; no angina or elevation of serum enzymes; or angina requiring hospitalization without surgery
^5 Seven cases were fatal; three in the placebo group and four in the tamoxifen group
^6 Three cases in the tamoxifen group were fatal
^7 All but three cases in each group required hospitalization
^8 Based on women without cataracts at baseline (6,230-Placebo, 6,199-tamoxifen)
^9 All women (6,707-Placebo, 6,681-tamoxifen)
^10 Updated long-term follow-up data (median 6.9 years) from NSABP P-1 study added after cut-off for the other information in this table.

Table 4 describes the characteristics of the breast cancers in the NSABP P-1 trial and includes tumor size, nodal status, ER status. Tamoxifen decreased the incidence of small estrogen receptor positive tumors, but did not alter the incidence of estrogen receptor negative tumors or larger tumors.

Table 4: Characteristics of Breast Cancer in NSABP P-1 Trial
Staging Parameter | Placebo; N=156 | Tamoxifen; N=86 | Total; N=242
Tumor Size:
T1 | 117 | 60 | 177
T2 | 28 | 20 | 48
T3 | 7 | 3 | 10
T4 | 1 | 2 | 3
Unknown | 3 | 1 | 4
Nodal Status:
Negative | 103 | 56 | 159
1 to 3 positive nodes | 29 | 14 | 43
≥ 4 positive nodes | 10 | 12 | 22
Unknown | 14 | 4 | 18
Stage:
I | 88 | 47 | 135
II: node negative | 15 | 9 | 24
II: node positive | 33 | 22 | 55
III | 6 | 4 | 10
IV | 2^1 | 1 | 3
Unknown | 12 | 3 | 15
Estrogen receptor:
Positive | 115 | 38 | 153
Negative | 27 | 36 | 63
Unknown | 14 | 12 | 26
^1 One participant presented with a suspicious bone scan but did not have documented metastases. She subsequently died of metastatic breast cancer.

Interim results from 2 trials in addition to the NSABP P-1 trial examining the effects of tamoxifen in reducing breast cancer incidence have been reported.

The first was the Italian Tamoxifen Prevention trial. In this trial women between the ages of 35 and 70, who had had a total hysterectomy, were randomized to receive 20 mg tamoxifen or matching placebo for 5 years. The primary endpoints were occurrence of, and death from, invasive breast cancer. Women without any specific risk factors for breast cancer were to be entered. Between 1992 and 1997, 5408 women were randomized. Hormone Replacement Therapy (HRT) was used in 14% of participants. The trial closed in 1997 due to the large number of dropouts during the first year of treatment (26%). After 46 months of follow-up there were 22 breast cancers in women on placebo and 19 in women on tamoxifen. Although no decrease in breast cancer incidence was observed, there was a trend for a reduction in breast cancer among women receiving protocol therapy for at least 1 year (19-placebo, 11-tamoxifen). The small numbers of participants along with the low level of risk in this otherwise healthy group precluded an adequate assessment of the effect of tamoxifen in reducing the incidence of breast cancer.

The second trial, the Royal Marsden Trial (RMT) was reported as an interim analysis. The RMT was begun in 1986 as a feasibility study of whether larger scale trials could be mounted. The trial was subsequently extended to a pilot trial to accrue additional participants to further assess the safety of tamoxifen. Twenty-four hundred and seventy-one women were entered between 1986 and 1996; they were selected on the basis of a family history of breast cancer. HRT was used in 40% of participants. In this trial, with a 70-month median follow-up, 34 and 36 breast cancers (8 noninvasive, 4 on each arm) were observed among women on tamoxifen and placebo, respectively. Patients in this trial were younger than those in the NSABP P-1 trial and may have been more likely to develop ER (-) tumors, which are unlikely to be reduced in number by tamoxifen therapy. Although women were selected on the basis of family history and were thought to have a high risk of breast cancer, few events occurred, reducing the statistical power of the study. These factors are potential reasons why the RMT may not have provided an adequate assessment of the effectiveness of tamoxifen in reducing the incidence of breast cancer.

In these trials, an increased number of cases of deep-vein thrombosis, pulmonary embolus, stroke, and endometrial cancer were observed on the tamoxifen arm compared to the placebo arm. The frequency of events was consistent with the safety data observed in the NSABP P-1 trial.

McCune-Albright Syndrome:

A single, uncontrolled multicenter trial of tamoxifen 20 mg once a day was conducted in a heterogenous group of girls with McCune-Albright syndrome and precocious puberty manifested by physical signs of pubertal development, episodes of vaginal bleeding and/or advanced bone age (bone age of at least 12 months beyond chronological age). Twenty-eight female pediatric patients, aged 2 to 10 years, were treated for up to 12 months. Effect of treatment on frequency of vaginal bleeding, bone age advancement, and linear growth rate was assessed relative to prestudy baseline. Tamoxifen treatment was associated with a 50% reduction in frequency of vaginal bleeding episodes by patient or family report (mean annualized frequency of 3.56 episodes at baseline and 1.73 episodes on-treatment). Among the patients who reported vaginal bleeding during the pre-study period, 62% (13 out of 21 patients) reported no bleeding for a 6-month period and 33% (7 out of 21 patients) reported no vaginal bleeding for the duration of the trial. Not all patients improved on treatment and a few patients not reporting vaginal bleeding in the 6 months prior to enrollment reported menses on treatment. Tamoxifen therapy was associated with a reduction in mean rate of increase of bone age. Individual responses with regard to bone age advancement were highly heterogeneous. Linear growth rate was reduced during the course of tamoxifen treatment in a majority of patients (mean change of 1.68 cm/year relative to baseline; change from 7.47 cm/year at baseline to 5.79 cm/year on study). This change was not uniformly seen across all stages of bone maturity; all recorded response failures occurred in patients with bone ages less than 7 years at screening.

Mean uterine volume increased after 6 months of treatment and doubled at the end of the one-year study. A causal relationship has not been established; however, as an increase in the incidence of endometrial adenocarcinoma and uterine sarcoma has been noted in adults treated with tamoxifen (see BOXED WARNING), continued monitoring of McCune-Albright patients treated with tamoxifen for long-term uterine effects is recommended. The safety and efficacy of tamoxifen for girls aged 2 to 10 years with McCune-Albright syndrome and precocious puberty have not been studied beyond one year of treatment. The long-term effects of tamoxifen therapy in girls have not been established.

INDICATIONS AND USAGE

Metastatic Breast Cancer:

Tamoxifen citrate tablets, USP are effective in the treatment of metastatic breast cancer in women and men. In premenopausal women with metastatic breast cancer, tamoxifen is an alternative to oophorectomy or ovarian irradiation. Available evidence indicates that patients whose tumors are estrogen receptor positive are more likely to benefit from tamoxifen therapy.

Adjuvant Treatment of Breast Cancer:

Tamoxifen citrate tablets, USP are indicated for the treatment of node-positive breast cancer in women following total mastectomy or segmental mastectomy, axillary dissection, and breast irradiation. In some tamoxifen adjuvant studies, most of the benefit to date has been in the subgroup with four or more positive axillary nodes.

Tamoxifen citrate tablets, USP are indicated for the treatment of axillary node-negative breast cancer in women following total mastectomy or segmental mastectomy, axillary dissection, and breast irradiation.

The estrogen and progesterone receptor values may help to predict whether adjuvant tamoxifen therapy is likely to be beneficial.

Tamoxifen reduces the occurrence of contralateral breast cancer in patients receiving adjuvant tamoxifen therapy for breast cancer.

Ductal Carcinoma in Situ (DCIS):

In women with DCIS, following breast surgery and radiation, tamoxifen citrate tablets are indicated to reduce the risk of invasive breast cancer (see BOXED WARNING at the beginning of the label). The decision regarding therapy with tamoxifen for the reduction in breast cancer incidence should be based upon an individual assessment of the benefits and risks of tamoxifen therapy.

Current data from clinical trials support 5 years of adjuvant tamoxifen therapy for patients with breast cancer.

Reduction in Breast Cancer Incidence in High Risk Women:

Tamoxifen citrate tablets are indicated to reduce the incidence of breast cancer in women at high risk for breast cancer. This effect was shown in a study of 5 years planned duration with a median follow-up of 4.2 years. Twenty-five percent of the participants received drug for 5 years. The longer-term effects are not known. In this study, there was no impact of tamoxifen on overall or breast cancer-related mortality (see BOXED WARNING at the beginning of the label).

Tamoxifen citrate tablets are indicated only for high-risk women. “High risk” is defined as women at least 35 years of age with a 5-year predicted risk of breast cancer ≥1.67%, as calculated by the Gail Model.

Examples of combinations of factors predicting a 5-year risk ≥1.67% are:

Age 35 or older and any of the following combination of factors:

- One first degree relative with a history of breast cancer, 2 or more benign biopsies, and a history of a breast biopsy showing atypical hyperplasia; or
- At least 2 first degree relatives with a history of breast cancer, and a personal history of at least one breast biopsy; or
- LCIS

Age 40 or older and any of the following combination of factors:

- One first degree relative with a history of breast cancer, 2 or more benign biopsies, age at first live birth 25 or older, and age at menarche 11 or younger; or
- At least 2 first degree relatives with a history of breast cancer, and age at first live birth 19 or younger; or
- One first degree relative with a history of breast cancer, and a personal history of a breast biopsy showing atypical hyperplasia.

Age 45 or older and any of the following combination of factors:

- At least 2 first degree relatives with a history of breast cancer and age at first live birth 24 or younger; or
- One first degree relative with a history of breast cancer with a personal history of a benign breast biopsy, age at menarche 11 or less and age at first live birth 20 or more.

Age 50 or older and any of the following combination of factors:

- At least 2 first degree relatives with a history of breast cancer; or
- History of 1 breast biopsy showing atypical hyperplasia, and age at first live birth 30 or older and age at menarche 11 or less; or
- History of at least 2 breast biopsies with a history of atypical hyperplasia, and age at first live birth 30 or more.

Age 55 or older and any of the following combination of factors:

- One first degree relative with a history of breast cancer with a personal history of a benign breast biopsy, and age at menarche 11 or less; or
- History of at least 2 breast biopsies with a history of atypical hyperplasia, and age at first live birth 20 or older.

Age 60 or older and:

- Five-year predicted risk of breast cancer ≥1.67%, as calculated by the Gail Model.

For women whose risk factors are not described in the above examples, the Gail Model is necessary to estimate absolute breast cancer risk. Health Care Professionals can obtain a Gail Model Risk Assessment Tool by dialing 1-888-838-2872.

There are insufficient data available regarding the effect of tamoxifen on breast cancer incidence in women with inherited mutations (BRCA1, BRCA2) to be able to make specific recommendations on the effectiveness of tamoxifen citrate in these patients.

After an assessment of the risk of developing breast cancer, the decision regarding therapy with tamoxifen for the reduction in breast cancer incidence should be based upon an individual assessment of the benefits and risks of tamoxifen citrate therapy. In the NSABP P-1 trial, tamoxifen treatment lowered the risk of developing breast cancer during the follow-up period of the trial, but did not eliminate breast cancer risk (see Table 3 in CLINICAL PHARMACOLOGY).

CONTRAINDICATIONS

Tamoxifen citrate tablets are contraindicated in patients with known hypersensitivity to the drug or any of its ingredients.

Reduction in Breast Cancer Incidence in High Risk Women and Women with DCIS:

Tamoxifen citrate tablets are contraindicated in women who require concomitant coumarin-type anticoagulant therapy or in women with a history of deep-vein thrombosis or pulmonary embolus.

WARNINGS

Effects in Metastatic Breast Cancer Patients:

As with other additive hormonal therapy (estrogens and androgens), hypercalcemia has been reported in some breast cancer patients with bone metastases within a few weeks of starting treatment with tamoxifen. If hypercalcemia does occur, appropriate measures should be taken and, if severe, tamoxifen should be discontinued.

Effects on the Uterus-Endometrial Cancer and Uterine Sarcoma:

An increased incidence of uterine malignancies has been reported in association with tamoxifen treatment. The underlying mechanism is unknown, but may be related to the estrogen-like effect of tamoxifen. Most uterine malignancies seen in association with tamoxifen are classified as adenocarcinoma of the endometrium. However, rare uterine sarcomas, including malignant mixed mullerian tumors (MMMT), have also been reported. Uterine sarcoma is generally associated with a higher FIGO stage (III/IV) at diagnosis, poorer prognosis, and shorter survival. Uterine sarcoma has been reported to occur more frequently among long-term users (≥2 years) of tamoxifen citrate than non-users. Some of the uterine malignancies (endometrial carcinoma or uterine sarcoma) have been fatal.

In the NSABP P-1 trial, among participants randomized to tamoxifen there was a statistically significant increase in the incidence of endometrial cancer (33 cases of invasive endometrial cancer, compared to 14 cases among participants randomized to placebo (RR=2.48, 95% CI: 1.27 to 4.92). The 33 cases in participants receiving tamoxifen were FIGO Stage I, including 20 IA, 12 IB, and 1 IC endometrial adenocarcinomas. In participants randomized to placebo, 13 were FIGO Stage I (8 IA and 5 IB) and 1 was FIGO Stage IV. Five women on tamoxifen citrate and 1 on placebo received postoperative radiation therapy in addition to surgery. This increase was primarily observed among women at least 50 years of age at the time of randomization (26 cases of invasive endometrial cancer, compared to 6 cases among participants randomized to placebo (RR=4.50, 95% CI: 1.78 to 13.16). Among women ≤49 years of age at the time of randomization there were 7 cases of invasive endometrial cancer, compared to 8 cases among participants randomized to placebo (RR=0.94, 95% CI: 0.28 to 2.89). If age at the time of diagnosis is considered, there were 4 cases of endometrial cancer among participants ≤49 randomized to tamoxifen compared to 2 among participants randomized to placebo (RR=2.21, 95% CI: 0.4 to 12.0). For women ≥50 at the time of diagnosis, there were 29 cases among participants randomized to tamoxifen compared to 12 among women on placebo (RR=2.5, 95% CI: 1.3 to 4.9). The risk ratios were similar in the two groups, although fewer events occurred in younger women. Most (29 of 33 cases in the tamoxifen group) endometrial cancers were diagnosed in symptomatic women, although 5 of 33 cases in the tamoxifen group occurred in asymptomatic women. Among women receiving tamoxifen the events appeared between 1 and 61 months (average=32 months) from the start of treatment.

In an updated review of long-term data (median length of total follow-up is 6.9 years, including blinded follow-up) on 8,306 women with an intact uterus at randomization in the NSABP P-1 risk reduction trial, the incidence of both adenocarcinomas and rare uterine sarcomas was increased in women taking tamoxifen. During blinded follow-up, there were 36 cases of FIGO Stage I endometrial adenocarcinoma (22 were FIGO Stage IA, 13 IB, and 1 IC) in women receiving tamoxifen and 15 cases in women receiving placebo [14 were FIGO Stage I (9 IA and 5 IB), and 1 case was FIGO Stage IV]. Of the patients receiving tamoxifen who developed endometrial cancer, one with Stage IA and 4 with Stage IB cancers received radiation therapy. In the placebo group, one patient with FIGO Stage IB cancer received radiation therapy and the patient with FIGO Stage IVB cancer received chemotherapy and hormonal therapy. During total follow-up, endometrial adenocarcinoma was reported in 53 women randomized to tamoxifen (30 cases of FIGO Stage IA, 20 were Stage IB, 1 was Stage IC, and 2 were Stage IIIC), and 17 women randomized to placebo (9 cases were FIGO Stage IA, 6 were Stage IB, 1 was Stage IIIC, and 1 was Stage IVB) (incidence per 1,000 women-years of 2.20 and 0.71, respectively). Some patients received post-operative radiation therapy in addition to surgery. Uterine sarcomas were reported in 4 women randomized to tamoxifen (1 was FIGO IA, 1 was FIGO IB, 1 was FIGO IIA, and 1 was FIGO IIIC) and 1 patient randomized to placebo (FIGO 1A); incidence per 1,000 women-years of 0.17 and 0.04, respectively. Of the patients randomized to tamoxifen, the FIGO IA and IB cases were a MMMT and sarcoma, respectively; the FIGO II was a MMMT; and the FIGO III was a sarcoma; and the 1 patient randomized to placebo had a MMMT. A similar increased incidence in endometrial adenocarcinoma and uterine sarcoma was observed among women receiving tamoxifen in 5 other NSABP clinical trials.

Any patient receiving or who has previously received tamoxifen who reports abnormal vaginal bleeding should be promptly evaluated. Patients receiving or who have previously received tamoxifen should have annual gynecological examinations and they should promptly inform their physicians if they experience any abnormal gynecological symptoms, e.g., menstrual irregularities, abnormal vaginal bleeding, changes in vaginal discharge, or pelvic pain or pressure.

In the P-1 trial, endometrial sampling did not alter the endometrial cancer detection rate compared to women who did not undergo endometrial sampling (0.6% with sampling, 0.5% without sampling) for women with an intact uterus. There are no data to suggest that routine endometrial sampling in asymptomatic women taking tamoxifen to reduce the incidence of breast cancer would be beneficial.

Non-Malignant Effects on the Uterus:

An increased incidence of endometrial changes including hyperplasia and polyps have been reported in association with tamoxifen treatment. The incidence and pattern of this increase suggest that the underlying mechanism is related to the estrogenic properties of tamoxifen.

There have been a few reports of endometriosis and uterine fibroids in women receiving tamoxifen. The underlying mechanism may be due to the partial estrogenic effect of tamoxifen. Ovarian cysts have also been observed in a small number of premenopausal patients with advanced breast cancer who have been treated with tamoxifen.

Tamoxifen has been reported to cause menstrual irregularity or amenorrhea.

Thromboembolic Effects of Tamoxifen:

There is evidence of an increased incidence of thromboembolic events, including deep-vein thrombosis and pulmonary embolism, during tamoxifen therapy. When tamoxifen is coadministered with chemotherapy, there may be a further increase in the incidence of thromboembolic effects. For treatment of breast cancer, the risks and benefits of tamoxifen should be carefully considered in women with a history of thromboembolic events. In a small substudy (N=81) of the NSABP P-1 trial, there appeared to be no benefit to screening women for Factor V Leiden and Prothrombin mutations G20210A as a means to identify those who may not be appropriate candidates for tamoxifen therapy.

Data from the NSABP P-1 trial show that participants receiving tamoxifen without a history of pulmonary emboli (PE) had a statistically significant increase in pulmonary emboli (18-tamoxifen, 6-placebo; RR=3.01, 95% CI: 1.15 to 9.27). Three of the pulmonary emboli, all in the tamoxifen arm, were fatal. Eighty-seven percent of the cases of pulmonary embolism occurred in women at least 50 years of age at randomization. Among women receiving tamoxifen, the events appeared between 2 and 60 months (average = 27 months) from the start of treatment.

In this same population, a non-statistically significant increase in deep-vein thrombosis (DVT) was seen in the tamoxifen group (30-tamoxifen, 19-placebo; RR=1.59, 95% CI: 0.86 to 2.98). The same increase in relative risk was seen in women ≤49 and in women ≥50, although fewer events occurred in younger women. Women with thromboembolic events were at risk for a second related event (7 out of 25 women on placebo, 5 out of 48 women on tamoxifen) and were at risk for complications of the event and its treatment (0/25 on placebo, 4/48 on tamoxifen). Among women receiving tamoxifen, deep-vein thrombosis events occurred between 2 and 57 months (average = 19 months) from the start of treatment.

There was a non-statistically significant increase in stroke among patients randomized to tamoxifen (24-Placebo; 34-tamoxifen; RR=1.42; 95% CI: 0.82 to 2.51). Six of the 24 strokes in the placebo group were considered hemorrhagic in origin and 10 of the 34 strokes in the tamoxifen group were categorized as hemorrhagic. Seventeen of the 34 strokes in the tamoxifen group were considered occlusive and 7 were considered to be of unknown etiology. Fourteen of the 24 strokes on the placebo arm were reported to be occlusive and 4 of unknown etiology. Among these strokes 3 strokes in the placebo group and 4 strokes in the tamoxifen group were fatal. Eighty-eight percent of the strokes occurred in women at least 50 years of age at the time of randomization. Among women receiving tamoxifen, the events occurred between 1 and 63 months (average = 30 months) from the start of treatment.

Effects on the Liver: Liver Cancer:

In the Swedish trial using adjuvant tamoxifen 40 mg/day for 2 to 5 years, 3 cases of liver cancer have been reported in the tamoxifen-treated group vs. 1 case in the observation group (see PRECAUTIONS, Carcinogenesis). In other clinical trials evaluating tamoxifen, no cases of liver cancer have been reported to date.

One case of liver cancer was reported in NSABP P-1 in a participant randomized to tamoxifen.

Effects on the Liver: Non-Malignant Effects:

Tamoxifen has been associated with changes in liver enzyme levels, and on rare occasions, a spectrum of more severe liver abnormalities including fatty liver, cholestasis, hepatitis and hepatic necrosis. A few of these serious cases included fatalities. In most reported cases the relationship to tamoxifen is uncertain. However, some positive rechallenges and dechallenges have been reported.

In the NSABP P-1 trial, few grade 3 to 4 changes in liver function (SGOT, SGPT, bilirubin, alkaline phosphatase) were observed (10 on placebo and 6 on tamoxifen). Serum lipids were not systematically collected.

Other Cancers:

A number of second primary tumors, occurring at sites other than the endometrium, have been reported following the treatment of breast cancer with tamoxifen in clinical trials. Data from the NSABP B-14 and P-1 studies show no increase in other (non-uterine) cancers among patients receiving tamoxifen. Whether an increased risk for other (non-uterine) cancers is associated with tamoxifen is still uncertain and continues to be evaluated.

Effects on the Eye:

Ocular disturbances, including corneal changes, decrement in color vision perception, retinal vein thrombosis, and retinopathy have been reported in patients receiving tamoxifen. An increased incidence of cataracts and the need for cataract surgery have been reported in patients receiving tamoxifen.

In the NSABP P-1 trial, an increased risk of borderline significance of developing cataracts among those women without cataracts at baseline (540-tamoxifen; 483-placebo; RR=1.13, 95% CI: 1.00 to 1.28) was observed. Among these same women, tamoxifen was associated with an increased risk of having cataract surgery (101-tamoxifen; 63-placebo; RR=1.62, 95% CI: 1.18 to 2.22) (see Table 3 in CLINICAL PHARMACOLOGY). Among all women on the trial (with or without cataracts at baseline), tamoxifen was associated with an increased risk of having cataract surgery (201-tamoxifen; 129-placebo; RR=1.58, 95% CI: 1.26 to 1.97). Eye examinations were not required during the study. No other conclusions regarding non-cataract ophthalmic events can be made.

Pregnancy Category D:

Tamoxifen may cause fetal harm when administered to a pregnant woman. Women should be advised not to become pregnant while taking tamoxifen or within 2 months of discontinuing tamoxifen and should use barrier or nonhormonal contraceptive measures if sexually active. Tamoxifen does not cause infertility, even in the presence of menstrual irregularity. Effects on reproductive functions are expected from the antiestrogenic properties of the drug. In reproductive studies in rats at dose levels equal to or below the human dose, nonteratogenic developmental skeletal changes were seen and were found reversible. In addition, in fertility studies in rats and in teratology studies in rabbits using doses at or below those used in humans, a lower incidence of embryo implantation and a higher incidence of fetal death or retarded in utero growth were observed, with slower learning behavior in some rat pups when compared to historical controls. Several pregnant marmosets were dosed with 10 mg/kg/day (about 2-fold the daily maximum recommended human dose on a mg/m^2 basis) during organogenesis or in the last half of pregnancy. No deformations were seen and, although the dose was high enough to terminate pregnancy in some animals, those that did maintain pregnancy showed no evidence of teratogenic malformations.

In rodent models of fetal reproductive tract development, tamoxifen (at doses 0.002 to 2.4-fold the daily maximum recommended human dose on a mg/m^2 basis) caused changes in both sexes that are similar to those caused by estradiol, ethynylestradiol and diethylstilbestrol. Although the clinical relevance of these changes is unknown, some of these changes, especially vaginal adenosis, are similar to those seen in young women who were exposed to diethylstilbestrol in utero and who have a 1 in 1,000 risk of developing clear-cell adenocarcinoma of the vagina or cervix. To date, in utero exposure to tamoxifen has not been shown to cause vaginal adenosis, or clear-cell adenocarcinoma of the vagina or cervix, in young women. However, only a small number of young women have been exposed to tamoxifen in utero, and a smaller number have been followed long enough (to age 15 to 20) to determine whether vaginal or cervical neoplasia could occur as a result of this exposure.

There are no adequate and well-controlled trials of tamoxifen in pregnant women. There have been a small number of reports of vaginal bleeding, spontaneous abortions, birth defects, and fetal deaths in pregnant women. If this drug is used during pregnancy, or the patient becomes pregnant while taking this drug, or within approximately two months after discontinuing therapy, the patient should be apprised of the potential risks to the fetus including the potential long-term risk of a DES-like syndrome.

Reduction in Breast Cancer Incidence in High Risk Women

Pregnancy Category D:

For sexually active women of child-bearing potential, tamoxifen therapy should be initiated during menstruation. In women with menstrual irregularity, a negative B-HCG immediately prior to the initiation of therapy is sufficient (see PRECAUTIONS, Information for Patients, Reduction in Breast Cancer Incidence in High Risk Women).

PRECAUTIONS

General:

Decreases in platelet counts, usually to 50,000 to 100,000/mm^3, infrequently lower, have been occasionally reported in patients taking tamoxifen for breast cancer. In patients with significant thrombocytopenia, rare hemorrhagic episodes have occurred, but it is uncertain if these episodes are due to tamoxifen therapy. Leukopenia has been observed, sometimes in association with anemia and/or thrombocytopenia. There have been rare reports of neutropenia and pancytopenia in patients receiving tamoxifen; this can sometimes be severe.

In the NSABP P-1 trial, 6 women on tamoxifen citrate and 2 on placebo experienced grade 3 to 4 drops in platelet counts (≤50,000/mm^3).

Information for Patients:

Patients should be instructed to read the Medication Guide supplied as required by law when tamoxifen citrate is dispensed. The complete text of the Medication Guide is reprinted at the end of this document.

Reduction in Invasive Breast Cancer and DCIS in Women with DCIS: Women with DCIS treated with lumpectomy and radiation therapy who are considering tamoxifen to reduce the incidence of a second breast cancer event should assess the risks and benefits of therapy, since treatment with tamoxifen decreased the incidence of invasive breast cancer, but has not been shown to affect survival (see Table 1 in CLINICAL PHARMACOLOGY).

Reduction in Breast Cancer Incidence in High Risk Women: Women who are at high risk for breast cancer can consider taking tamoxifen therapy to reduce the incidence of breast cancer. Whether the benefits of treatment are considered to outweigh the risks depends on a woman's personal health history and on how she weighs the benefits and risks. Tamoxifen therapy to reduce the incidence of breast cancer may therefore not be appropriate for all women at high risk for breast cancer. Women who are considering tamoxifen therapy should consult their health care professional for an assessment of the potential benefits and risks prior to starting therapy for reduction in breast cancer incidence (see Table 3 in CLINICAL PHARMACOLOGY). Women should understand that tamoxifen reduces the incidence of breast cancer, but may not eliminate risk. Tamoxifen decreased the incidence of small estrogen receptor positive tumors, but did not alter the incidence of estrogen receptor negative tumors or larger tumors. In women with breast cancer who are at high risk of developing a second breast cancer, treatment with about 5 years of tamoxifen reduced the annual incidence rate of a second breast cancer by approximately 50%.

Women who are pregnant or who plan to become pregnant should not take tamoxifen to reduce their risk of breast cancer. Effective nonhormonal contraception must be used by all premenopausal women taking tamoxifen and for approximately two months after discontinuing therapy if they are sexually active. Tamoxifen does not cause infertility, even in the presence of menstrual irregularity. For sexually active women of child-bearing potential, tamoxifen therapy should be initiated during menstruation. In women with menstrual irregularity, a negative B-HCG immediately prior to the initiation of therapy is sufficient (see WARNINGS, Pregnancy Category D).

Two European trials of tamoxifen to reduce the risk of breast cancer were conducted and showed no difference in the number of breast cancer cases between the tamoxifen and placebo arms. These studies had trial designs that differed from that of NSABP P-1, were smaller than NSABP P-1, and enrolled women at a lower risk for breast cancer than those in P-1.

Monitoring During Tamoxifen Citrate Therapy: Women taking or having previously taken tamoxifen should be instructed to seek prompt medical attention for new breast lumps, vaginal bleeding, gynecologic symptoms (menstrual irregularities, changes in vaginal discharge, or pelvic pain or pressure), symptoms of leg swelling or tenderness, unexplained shortness of breath, or changes in vision. Women should inform all care providers, regardless of the reason for evaluation, that they take tamoxifen.

Women taking tamoxifen to reduce the incidence of breast cancer should have a breast examination, a mammogram, and a gynecologic examination prior to the initiation of therapy. These studies should be repeated at regular intervals while on therapy, in keeping with good medical practice. Women taking tamoxifen as adjuvant breast cancer therapy should follow the same monitoring procedures as for women taking tamoxifen for the reduction in the incidence of breast cancer. Women taking tamoxifen as treatment for metastatic breast cancer should review this monitoring plan with their care provider and select the appropriate modalities and schedule of evaluation.

Laboratory Tests:

Periodic complete blood counts, including platelet counts, and periodic liver function tests should be obtained.

During the ATAC trial, more patients receiving anastrozole were reported to have an elevated serum cholesterol compared to patients receiving tamoxifen citrate (9% versus 3.5%, respectively).

Drug Interactions:

When tamoxifen is used in combination with coumarin-type anticoagulants, a significant increase in anticoagulant effect may occur. Where such coadministration exists, careful monitoring of the patient's prothrombin time is recommended.

In the NSABP P-1 trial, women who required coumarin-type anticoagulants for any reason were ineligible for participation in the trial (see CONTRAINDICATIONS).

There is an increased risk of thromboembolic events occurring when cytotoxic agents are used in combination with tamoxifen.

Tamoxifen reduced letrozole plasma concentrations by 37%. The effect of tamoxifen on metabolism and excretion of other antineoplastic drugs, such as cyclophosphamide and other drugs that require mixed function oxidases for activation, is not known. Tamoxifen and N-desmethyl tamoxifen plasma concentrations have been shown to be reduced when coadministered with rifampin or aminoglutethimide. Induction of CYP3A4-mediated metabolism is considered to be the mechanism by which these reductions occur; other CYP3A4 inducing agents have not been studied to confirm this effect.

One patient receiving tamoxifen with concomitant phenobarbital exhibited a steady-state serum level of tamoxifen lower than that observed for other patients (i.e., 26 ng/mL vs. mean value of 122 ng/mL). However, the clinical significance of this finding is not known. Rifampin induced the metabolism of tamoxifen and significantly reduced the plasma concentrations of tamoxifen in 10 patients. Aminoglutethimide reduces tamoxifen and N-desmethyl tamoxifen plasma concentrations. Medroxyprogesterone reduces plasma concentrations of N-desmethyl, but not tamoxifen.

Concomitant bromocriptine therapy has been shown to elevate serum tamoxifen and N-desmethyl tamoxifen.

Based on clinical and pharmacokinetic results from the anastrozole adjuvant trial, tamoxifen citrate should not be administered with anastrozole (see CLINICAL PHARMACOLOGY, Drug-Drug Interactions).

Drug/Laboratory Testing Interactions:

During postmarketing surveillance, T4 elevations were reported for a few postmenopausal patients which may be explained by increases in thyroid-binding globulin. These elevations were not accompanied by clinical hyperthyroidism.

Variations in the karyopyknotic index on vaginal smears and various degrees of estrogen effect on Pap smears have been infrequently seen in postmenopausal patients given tamoxifen.

In the postmarketing experience with tamoxifen, infrequent cases of hyperlipidemias have been reported. Periodic monitoring of plasma triglycerides and cholesterol may be indicated in patients with pre-existing hyperlipidemias (see ADVERSE REACTIONS, Postmarketing Experience).

Carcinogenesis:

A conventional carcinogenesis study in rats at doses of 5, 20, and 35 mg/kg/day (about one, three and seven-fold the daily maximum recommended human dose on a mg/m^2 basis) administered by oral gavage for up to 2 years revealed a significant increase in hepatocellular carcinoma at all doses. The incidence of these tumors was significantly greater among rats administered 20 or 35 mg/kg/day (69%) compared to those administered 5 mg/kg/day (14%). In a separate study, rats were administered tamoxifen at 45 mg/kg/day (about nine-fold the daily maximum recommended human dose on a mg/m^2 basis); hepatocellular neoplasia was exhibited at 3 to 6 months.

Granulosa cell ovarian tumors and interstitial cell testicular tumors were observed in 2 separate mouse studies. The mice were administered the trans and racemic forms of tamoxifen for 13 to 15 months at doses of 5, 20 and 50 mg/kg/day (about one-half, two, and five-fold the daily recommended human dose on a mg/m^2 basis).

Mutagenesis:

No genotoxic potential was found in a conventional battery of in vivo and in vitro tests with pro- and eukaryotic test systems with drug metabolizing systems. However, increased levels of DNA adducts were observed by ^32P post-labeling in DNA from rat liver and cultured human lymphocytes. Tamoxifen also has been found to increase levels of micronucleus formation in vitro in human lymphoblastoid cell line (MCL-5). Based on these findings, tamoxifen is genotoxic in rodent and human MCL-5 cells.

Impairment of Fertility:

Tamoxifen produced impairment of fertility and conception in female rats at doses of 0.04 mg/kg/day (about 0.01-fold the daily maximum recommended human dose on a mg/m^2 basis) when dosed for two weeks prior to mating through day 7 of pregnancy. At this dose, fertility and reproductive indices were markedly reduced with total fetal mortality. Fetal mortality was also increased at doses of 0.16 mg/kg/day (about 0.03-fold the daily maximum recommended human dose on a mg/m^2 basis) when female rats were dosed from days 7 to 17 of pregnancy. Tamoxifen produced abortion, premature delivery and fetal death in rabbits administered doses equal to or greater than 0.125 mg/kg/day (about 0.05-fold the daily maximum recommended human dose on a mg/m^2 basis). There were no teratogenic changes in either rats or rabbits.

Pregnancy Category D:

See WARNINGS.

Nursing Mothers:

Tamoxifen has been reported to inhibit lactation. Two placebo-controlled studies in over 150 women have shown that tamoxifen significantly inhibits early postpartum milk production. In both studies tamoxifen was administered within 24 hours of delivery for between 5 and 18 days. The effect of tamoxifen on established milk production is not known.

There are no data that address whether tamoxifen is excreted into human milk. If excreted, there are no data regarding the effects of tamoxifen in breast milk on the breastfed infant or breastfed animals. However, direct neonatal exposure of tamoxifen to mice and rats (not via breast milk) produced 1) reproductive tract lesions in female rodents (similar to those seen in humans after intrauterine exposure to diethylstilbestrol) and 2) functional defects of the reproductive tract in male rodents such as testicular atrophy and arrest of spermatogenesis.

It is not known if tamoxifen citrate is excreted in human milk. Because of the potential for serious adverse reactions in nursing infants from tamoxifen, women taking tamoxifen should not breast feed.

Reduction in Breast Cancer Incidence in High Risk Women with DCIS:

It is not known if tamoxifen is excreted in human milk. Because of the potential for serious adverse reactions in nursing infants from tamoxifen, women taking tamoxifen should not breast feed.

Pediatric Use:

The safety and efficacy of tamoxifen for girls aged 2 to 10 years with McCune-Albright syndrome and precocious puberty have not been studied beyond one year of treatment. The long-term effects of tamoxifen therapy for girls have not been established. In adults treated with tamoxifen, an increase in incidence of uterine malignancies, stroke and pulmonary embolism has been noted (see BOXED WARNING and CLINICAL PHARMACOLOGY, Clinical Studies, McCune-Albright Syndrome subsection).

Geriatric Use:

In the NSABP P-1 trial, the percentage of women at least 65 years of age was 16%. Women at least 70 years of age accounted for 6% of the participants. A reduction in breast cancer incidence was seen among participants in each of the subsets. A total of 28 and 10 invasive breast cancers were seen among participants 65 and older in the placebo and tamoxifen groups, respectively. Across all other outcomes, the results in this subset reflect the results observed in the subset of women at least 50 years of age. No overall differences in tolerability were observed between older and younger patients (see CLINICAL PHARMACOLOGY, Clinical Studies, Reduction in Breast Cancer Incidence in High Risk Women).

In the NSABP B-24 trial, the percentage of women at least 65 years of age was 23%. Women at least 70 years of age accounted for 10% of participants. A total of 14 and 12 invasive breast cancers were seen among participants 65 and older in the placebo and tamoxifen groups, respectively. This subset is too small to reach any conclusions on efficacy. Across all other endpoints, the results in this subset were comparable to those of younger women enrolled in this trial. No overall differences in tolerability were observed between older and younger patients.

ADVERSE REACTIONS

Adverse reactions to tamoxifen are relatively mild and rarely severe enough to require discontinuation of treatment in breast cancer patients.

Continued clinical studies have resulted in further information which better indicates the incidence of adverse reactions with tamoxifen as compared to placebo.

Metastatic Breast Cancer:

Increased bone and tumor pain and, also, local disease flare have occurred, which are sometimes associated with a good tumor response. Patients with increased bone pain may require additional analgesics. Patients with soft tissue disease may have sudden increases in the size of preexisting lesions, sometimes associated with marked erythema within and surrounding the lesions and/or the development of new lesions. When they occur, the bone pain or disease flare are seen shortly after starting tamoxifen and generally subside rapidly.

In patients treated with tamoxifen for metastatic breast cancer, the most frequent adverse reaction to tamoxifen is hot flashes.

Other adverse reactions which are seen infrequently are hypercalcemia, peripheral edema, distaste for food, pruritus vulvae, depression, dizziness, light-headedness, headache, hair thinning and/or partial hair loss, and vaginal dryness.

Premenopausal Women:

The following table summarizes the incidence of adverse reactions reported at a frequency of 2% or greater from clinical trials (Ingle, Pritchard, Buchanan) which compared tamoxifen therapy to ovarian ablation in premenopausal patients with metastatic breast cancer.

 | TAMOXIFEN; All Effects; % of Women | OVARIAN ABLATION; All Effects; % of Women
Adverse Reactions* | n=104 | n=100
Flush | 33 | 46
Amenorrhea | 16 | 69
Altered Menses | 13 | 5
Oligomenorrhea | 9 | 1
Bone Pain | 6 | 6
Menstrual Disorder | 6 | 4
Nausea | 5 | 4
Cough/Coughing | 4 | 1
Edema | 4 | 1
Fatigue | 4 | 1
Musculoskeletal Pain | 3 | 0
Pain | 3 | 4
Ovarian Cyst(s) | 3 | 2
Depression | 2 | 2
Abdominal Cramps | 1 | 2
Anorexia | 1 | 2
*Some women had more than one adverse reaction.

Male Breast Cancer:

Tamoxifen is well tolerated in males with breast cancer. Reports from the literature and case reports suggest that the safety profile of tamoxifen in males is similar to that seen in women. Loss of libido and impotence have resulted in discontinuation of tamoxifen therapy in male patients. Also, in oligospermic males treated with tamoxifen, LH, FSH, testosterone and estrogen levels were elevated. No significant clinical changes were reported.

Adjuvant Breast Cancer:

In the NSABP B-14 study, women with axillary node-negative breast cancer were randomized to 5 years of tamoxifen 20 mg/day or placebo following primary surgery. The reported adverse effects are tabulated below (mean follow-up of approximately 6.8 years) showing adverse events more common on tamoxifen than on placebo. The incidence of hot flashes (64% vs. 48%), vaginal discharge (30% vs. 15%), and irregular menses (25% vs. 19%) were higher with tamoxifen compared with placebo. All other adverse effects occurred with similar frequency in the 2 treatment groups, with the exception of thrombotic events; a higher incidence was seen in tamoxifen-treated patients (through 5 years, 1.7% vs. 0.4%). Two of the patients treated with tamoxifen who had thrombotic events died.

NSABP B-14 Study
Adverse Effect | % of Women
Adverse Effect | TAMOXIFEN; (n=1422) | PLACEBO; (n=1437)
Hot Flashes | 64 | 48
Fluid Retention | 32 | 30
Vaginal Discharge | 30 | 15
Nausea | 26 | 24
Irregular Menses | 25 | 19
Weight Loss (>5%) | 23 | 18
Skin Changes | 19 | 15
Increased SGOT | 5 | 3
Increased Bilirubin | 2 | 1
Increased Creatinine | 2 | 1
Thrombocytopenia* | 2 | 1
Thrombotic Events
Deep Vein Thrombosis | 0.8 | 0.2
Pulmonary Embolism | 0.5 | 0.2
Superficial Phlebitis | 0.4 | 0.0
*Defined as a platelet count of <100,000/mm^3

In the Eastern Cooperative Oncology Group (ECOG) adjuvant breast cancer trial, tamoxifen or placebo was administered for 2 years to women following mastectomy. When compared to placebo, tamoxifen showed a significantly higher incidence of hot flashes (19% vs. 8% for placebo). The incidence of all other adverse reactions was similar in the 2 treatment groups with the exception of thrombocytopenia where the incidence for tamoxifen was 10% vs. 3% for placebo, an observation of borderline statistical significance.

In other adjuvant studies, Toronto and Tamoxifen Adjuvant Trial Organization (NATO), women received either tamoxifen or no therapy. In the Toronto study, hot flashes were observed in 29% of patients for tamoxifen vs. 1% in the untreated group. In the NATO trial, hot flashes and vaginal bleeding were reported in 2.8%, and 2.0% of women, respectively, for tamoxifen vs. 0.2% for each in the untreated group.

Anastrozole Adjuvant Trial - Study of Anastrozole Compared to Tamoxifen for Adjuvant Treatment of Early Breast Cancer (see CLINICAL PHARMACOLOGY, Clinical Studies).

At a median follow-up of 33 months, the combination of anastrozole and tamoxifen citrate did not demonstrate any efficacy benefit when compared to tamoxifen therapy given alone in all patients as well as in the hormone receptor positive subpopulation. This treatment arm was discontinued from the trial. The median duration of adjuvant treatment for safety evaluation was 59.8 months and 59.6 months for patients receiving anastrozole 1 mg and tamoxifen 20 mg, respectively.

Adverse events occurring with an incidence of at least 5% in either treatment group during treatment or within 14 days of the end of treatment are presented in the following table.

Adverse events occurring with an incidence of at least 5% in either treatment group during treatment, or within 14 days of the end of treatment
Body system and adverse event by COSTART-preferred term* | Anastrozole; 1 mg; (N = 3092) | TAMOXIFEN; 20 mg; (N = 3094)
Body as a whole
Asthenia | 575 (19) | 544 (18)
Pain | 533 (17) | 485 (16)
Back pain | 321 (10) | 309 (10)
Headache | 314 (10) | 249 (8)
Abdominal pain | 271 (9) | 276 (9)
Infection | 285 (9) | 276 (9)
Accidental injury | 311 (10) | 303 (10)
Flu syndrome | 175 (6) | 195 (6)
Chest pain | 200 (7) | 150 (5)
Neoplasm | 162 (5) | 144 (5)
Cyst | 138 (5) | 162 (5)
Cardiovascular
Vasodilatation | 1104 (36) | 1264 (41)
Hypertension | 402 (13) | 349 (11)
Digestive
Nausea | 343 (11) | 335 (11)
Constipation | 249 (8) | 252 (8)
Diarrhea | 265 (9) | 216 (7)
Dyspepsia | 206 (7) | 169 (6)
Gastrointestinal disorder | 210 (7) | 158 (5)
Hemic and lymphatic
Lymphoedema | 304 (10) | 341 (11)
Anemia | 113 (4) | 159 (5)
Metabolic and nutritional
Peripheral edema | 311 (10) | 343 (11)
Weight gain | 285 (9) | 274 (9)
Hypercholesterolemia | 278 (9) | 108 (3.5)
Musculoskeletal
Arthritis | 512 (17) | 445 (14)
Arthralgia | 467 (15) | 344 (11)
Osteoporosis | 325 (11) | 226 (7)
Fracture | 315 (10) | 209 (7)
Bone pain | 201 (7) | 185 (6)
Arthrosis | 207 (7) | 156 (5)
Joint Disorder | 184 (6) | 160 (5)
Myalgia | 179 (6) | 160 (5)
Nervous system
Depression | 413 (13) | 382 (12)
Insomnia | 309 (10) | 281 (9)
Dizziness | 236 (8) | 234 (8)
Anxiety | 195 (6) | 180 (6)
Paraesthesia | 215 (7) | 145 (5)
Respiratory
Pharyngitis | 443 (14) | 422 (14)
Cough increased | 261 (8) | 287 (9)
Dyspnea | 234 (8) | 237 (8)
Sinusitis | 184 (6) | 159 (5)
Bronchitis | 167 (5) | 153 (5)
Skin and appendages
Rash | 333 (11) | 387 (13)
Sweating | 145 (5) | 177 (6)
Special Senses
Cataract specified | 182 (6) | 213 (7)
Urogenital
Leukorrhea | 86 (3) | 286 (9)
Urinary tract infection | 244 (8) | 313 (10)
Breast pain | 251 (8) | 169 (6)
Breast neoplasm | 164 (5) | 139 (5)
Vulvovaginitis | 194 (6) | 150 (5)
Vaginal hemorrhage† | 122 (4) | 180 (6)
Vaginitis | 125 (4) | 158 (5)
COSTART Coding Symbols for Thesaurus of Adverse Reaction Terms.
N = Number of patients receiving the treatment.
*A patient may have had more than 1 adverse event, including more than 1 adverse event in the same body system.
† Vaginal hemorrhage without further diagnosis.
** The combination arm was discontinued due to lack of efficacy benefit at 33 months of follow-up.

Certain adverse events and combinations of adverse events were prospectively specified for analysis, based on the known pharmacologic properties and side effect profiles of the two drugs (see the following table).

Number (%) of Patients with Pre-Specified Adverse Event in the Anastrozole Adjuvant Trial^1
 | Anastrozole; N=3092; (%) | TAMOXIFEN; N=3094; (%) | Odds-ratio^4 | 95% Cl^4
Hot Flashes | 1104 (36) | 1264 (41) | 0.80 | 0.73 to 0.89
Musculoskeletal Events^2 | 1100 (36) | 911 (29) | 1.32 | 1.19 to 1.47
Fatigue/Asthenia | 575 (19) | 544 (18) | 1.07 | 0.94 to 1.22
Mood Disturbances | 597 (19) | 554 (18) | 1.10 | 0.97 to 1.25
Nausea and Vomiting | 393 (13) | 384 (12) | 1.03 | 0.88 to 1.19
All Fractures | 315 (10) | 209 (7) | 1.57 | 1.30 to 1.88
Fractures of Spine, Hip, or Wrist | 133 (4) | 91 (3) | 1.48 | 1.13 to 1.95
Wrist/Colles’ fractures | 67 (2) | 50 (2)
Spine fractures | 43 (1) | 22 (1)
Hip fractures | 28 (1) | 26 (1)
Cataracts | 182 (6) | 213 (7) | 0.85 | 0.69 to 1.04
Vaginal Bleeding | 167 (5) | 317 (10) | 0.50 | 0.41 to 0.61
Ischemic Cardiovascular Disease | 127 (4) | 104 (3) | 1.23 | 0.95 to 1.60
Vaginal Discharge | 109 (4) | 408 (13) | 0.24 | 0.19 to 0.30
Venous Thromboembolic events | 87 (3) | 140 (5) | 0.61 | 0.47 to 0.80
Deep Venous Thromboembolic Events | 48 (2) | 74 (2) | 0.64 | 0.45 to 0.93
Ischemic Cerebrovascular Event | 62 (2) | 88 (3) | 0.70 | 0.50 to 0.97
Endometrial Cancer^3 | 4 (0.2) | 13 (0.6) | 0.31 | 0.10 to 0.94
^1 Patients with multiple events in the same category are counted only once in that category.
^2 Refers to joint symptoms, including joint disorder, arthritis, arthrosis and arthralgia.
^3 Percentages calculated based upon the numbers of patients with an intact uterus at baseline.
^4 The odds ratios < 1.00 favor Anastrozole and those > 1.00 favor tamoxifen.

Patients receiving anastrozole had an increase in joint disorders (including arthritis, arthrosis and arthralgia) compared with patients receiving tamoxifen. Patients receiving anastrozole had an increase in the incidence of all fractures (specifically fractures of spine, hip and wrist) [315 (10%)] compared with patients receiving tamoxifen [209 (7%)]. Patients receiving anastrozole had a decrease in hot flashes, vaginal bleeding, vaginal discharge, endometrial cancer, venous thromboembolic events and ischemic cerebrovascular events compared with patients receiving tamoxifen.

Patients receiving tamoxifen had a decrease in hypercholesterolemia (108 [3.5%]) compared to patients receiving anastrozole (278 [9%]). Angina pectoris was reported in 71 [2.3%] patients in the anastrozole arm and 51 [1.6%] patients in the tamoxifen arm; myocardial infarction was reported in 37 [1.2%] patients in the anastrozole arm and in 34 [1.1%] patients in the tamoxifen arm.

Results from the adjuvant trial bone substudy, at 12 and 24 months demonstrated that patients receiving anastrozole had a mean decrease in both lumbar spine and total hip bone mineral density (BMD) compared to baseline. Patients receiving tamoxifen had a mean increase in both lumbar spine and total hip BMD compared to baseline.

Ductal Carcinoma in Situ (DCIS):

The type and frequency of adverse events in the NSABP B-24 trial were consistent with those observed in the other adjuvant trials conducted with tamoxifen.

Reduction in Breast Cancer Incidence in High Risk Women:

In the NSABP P-1 trial, there was an increase in five serious adverse effects in the tamoxifen group: endometrial cancer (33 cases in the tamoxifen group vs. 14 in the placebo group); pulmonary embolism (18 cases in the tamoxifen group vs. 6 in the placebo group); deep-vein thrombosis (30 cases in the tamoxifen group vs. 19 in the placebo group); stroke (34 cases in the tamoxifen group vs. 24 in the placebo group); cataract formation (540 cases in the tamoxifen citrate group vs. 483 in the placebo group) and cataract surgery (101 cases in the tamoxifen group vs. 63 in the placebo group) (see WARNINGS and Table 3 in CLINICAL PHARMACOLOGY).

The following table presents the adverse events observed in NSABP P-1 by treatment arm. Only adverse events more common on tamoxifen than placebo are shown.

NSABP P-1 Trial: All Adverse Events
 | % of Women
 | TAMOXIFEN; N=6681 | PLACEBO; N=6707
Self Reported Symptoms | N=6441^1 | N=6469^1
Hot Flashes | 80 | 68
Vaginal Discharges | 55 | 35
Vaginal Bleeding | 23 | 22
Laboratory Abnormalities | N=6520^2 | N=6535^2
Platelets decreased | 0.7 | 0.3
Adverse Effects | N=6492^3 | N=6484^3
Other Toxicities
Mood | 11.6 | 10.8
Infection/Sepsis | 6.0 | 5.1
Constipation | 4.4 | 3.2
Alopecia | 5.2 | 4.4
Skin | 5.6 | 4.7
Allergy | 2.5 | 2.1
^1 Number with Quality of Life Questionnaires
^2 Number with Treatment Follow-up Forms
^3 Number with Adverse Drug Reaction Forms

In the NSABP P-1 trial, 15.0% and 9.7% of participants receiving tamoxifen and placebo therapy, respectively withdrew from the trial for medical reasons. The following are the medical reasons for withdrawing from tamoxifen and placebo therapy, respectively: hot flashes (3.1% vs. 1.5%) and vaginal discharge (0.5% vs. 0.1%).

In the NSABP P-1 trial, 8.7% and 9.6% of participants receiving tamoxifen citrate and placebo therapy, respectively withdrew for non-medical reasons.

On the NSABP P-1 trial, hot flashes of any severity occurred in 68% of women on placebo and in 80% of women on tamoxifen. Severe hot flashes occurred in 28% of women on placebo and 45% of women on tamoxifen. Vaginal discharge occurred in 35% and 55% of women on placebo and tamoxifen respectively; and was severe in 4.5% and 12.3% respectively. There was no difference in the incidence of vaginal bleeding between treatment arms.

Pediatric Patients

McCune-Albright Syndrome:

Mean uterine volume increased after 6 months of treatment and doubled at the end of the one-year study. A causal relationship has not been established; however, as an increase in the incidence of endometrial adenocarcinoma and uterine sarcoma has been noted in adults treated with tamoxifen (see BOXED WARNING), continued monitoring of McCune-Albright patients treated with tamoxifen for long-term effects is recommended. The safety and efficacy of tamoxifen for girls aged 2 to 10 years with McCune-Albright syndrome and precocious puberty have not been studied beyond 1 year of treatment. The long-term effects of tamoxifen therapy in girls have not been established.

Postmarketing Experience:

Less frequently reported adverse reactions are vaginal bleeding, vaginal discharge, menstrual irregularities, skin rash and headaches. Usually these have not been of sufficient severity to require dosage reduction or discontinuation of treatment. Very rare reports of erythema multiforme, Stevens-Johnson syndrome, bullous pemphigoid, interstitial pneumonitis, and rare reports of hypersensitivity reactions including angioedema have been reported with tamoxifen therapy. In some of these cases, the time to onset was more than one year. Rarely, elevation of serum triglyceride levels, in some cases with pancreatitis, may be associated with the use of tamoxifen (see PRECAUTIONS, Drug/Laboratory Testing Interactions).

To report SUSPECTED ADVERSE REACTIONS, contact Teva at 1-888-838-2872 or FDA at 1-800-FDA-1088 or www.fda.gov/medwatch.

OVERDOSAGE

Signs observed at the highest doses following studies to determine LD50 in animals were respiratory difficulties and convulsions.

Acute overdosage in humans has not been reported. In a study of advanced metastatic cancer patients which specifically determined the maximum tolerated dose of tamoxifen in evaluating the use of very high doses to reverse multidrug resistance, acute neurotoxicity manifested by tremor, hyperreflexia, unsteady gait and dizziness were noted. These symptoms occurred within 3 to 5 days of beginning tamoxifen and cleared within 2 to 5 days after stopping therapy. No permanent neurologic toxicity was noted. One patient experienced a seizure several days after tamoxifen was discontinued and neurotoxic symptoms had resolved. The causal relationship of the seizure to tamoxifen therapy is unknown. Doses given in these patients were all greater than 400 mg/m^2 loading dose, followed by maintenance doses of 150 mg/m^2 of tamoxifen given twice a day.

In the same study, prolongation of the QT interval on the electrocardiogram was noted when patients were given doses higher than 250 mg/m^2 loading dose, followed by maintenance doses of 80 mg/m^2 of tamoxifen given twice a day. For a woman with a body surface area of 1.5 m^2 the minimal loading dose and maintenance doses given at which neurological symptoms and QT changes occurred were at least 6 fold higher in respect to the maximum recommended dose.

No specific treatment for overdosage is known; treatment must be symptomatic.

DOSAGE AND ADMINISTRATION

For patients with breast cancer, the recommended daily dose is 20 to 40 mg. Dosages greater than 20 mg per day should be given in divided doses (morning and evening).

In three single agent adjuvant studies in women, one 10 mg tamoxifen citrate tablet was administered two (ECOG and NATO) or three (Toronto) times a day for two years. In the NSABP B-14 adjuvant study in women with node-negative breast cancer, one 10 mg tamoxifen citrate tablet was given twice a day for at least 5 years. Results of the B-14 study suggest that continuation of therapy beyond five years does not provide additional benefit (see CLINICAL PHARMACOLOGY). In the EBCTCG 1995 overview, the reduction in recurrence and mortality was greater in those studies that used tamoxifen for about 5 years than in those that used tamoxifen for a shorter period of therapy. There was no indication that doses greater than 20 mg per day were more effective. Current data from clinical trials support 5 years of adjuvant tamoxifen therapy for patients with breast cancer.

Ductal Carcinoma in Situ (DCIS):

The recommended dose is tamoxifen citrate tablets 20 mg daily for 5 years.

Reduction in Breast Cancer Incidence in High Risk Women:

The recommended dose is tamoxifen citrate tablets 20 mg daily for 5 years. There are no data to support the use of tamoxifen other than for 5 years (see CLINICAL PHARMACOLOGY, Clinical Studies, Reduction in Breast Cancer Incidence in High Risk Women).

HOW SUPPLIED

Tamoxifen Citrate Tablets, USP are available as:

10 mg: Containing 15.2 mg tamoxifen citrate USP, an amount equivalent to 10 mg of tamoxifen. White, round, unscored, biconvex tablet. Debossed with "2232" on one side and "WPI" on the other side.
Available in bottles of:
Unit-of-use 60 Tablets NDC 0591-2472-60
Unit-of-use 180 Tablets NDC 0591-2472-18

20 mg: Containing 30.4 mg tamoxifen citrate USP, an amount equivalent to 20 mg of tamoxifen. White, round, unscored, biconvex tablet. Debossed with "2233" on one side and "WPI" on the other side.
Available in bottles of:
Unit-of-use 30 Tablets NDC 0591-2473-30
Unit-of-use 90 Tablets NDC 0591-2473-19

Store at 20° to 25°C (68° to 77°F) [See USP Controlled Room Temperature].

Dispense in a well-closed, light-resistant container.

Keep this and all medications out of the reach of children.

For more information about tamoxifen citrate, call 1-888-838-2872.

Brands listed are the trademarks of their respective owners.

Manufactured For:

Teva Pharmaceuticals

Parsippany, NJ 07054

Rev. B 5/2025

MEDICATION GUIDE

Tamoxifen Citrate (ta mox′ i fen si′ trate) Tablets, USP

Written for women who use tamoxifen to lower their high chance of getting breast cancer or who have ductal carcinoma in situ (DCIS)

This Medication Guide discusses only the use of tamoxifen to lower the chance of getting breast cancer in high-risk women and in women treated for DCIS.

People taking tamoxifen to treat breast cancer have different benefits and different decisions to make than high-risk women or women with ductal carcinoma in situ (DCIS) taking tamoxifen to reduce the chance of getting breast cancer. If you already have breast cancer, talk with your doctor about how the benefits of treating breast cancer with tamoxifen compare to the risks that are described in this document.

Why should I read this Medication Guide?

This guide has information to help you decide whether to use tamoxifen to lower your chance of getting breast cancer.

You and your doctor should talk about whether the possible benefit of tamoxifen in lowering your high chance of getting breast cancer is greater than its possible risks. Your doctor has a special computer program or hand-held calculator to tell if you are in the high-risk group. If you have DCIS and have been treated with surgery and radiation therapy, your doctor may prescribe tamoxifen to decrease your chance of getting invasive (spreading) breast cancer.

Read this guide carefully before you start tamoxifen. It is important to read the information you get each time you get more medicine. There may be something new. This guide does not tell you everything about tamoxifen and does not take the place of talking with your doctor.

Only you and your doctor can determine if tamoxifen is right for you.

What is the most important information I should know about using tamoxifen to reduce the chance of getting breast cancer?

Tamoxifen is a prescription medicine that is like estrogen (female hormone) in some ways and different in other ways. In the breast, tamoxifen can block estrogen’s effects. Because it does this, tamoxifen may block the growth of breast cancers that need estrogen to grow (cancers that are estrogen- or progesterone-receptor positive).

Tamoxifen can lower the chance of getting breast cancer in women with a higher than normal chance of getting breast cancer in the next five years (high-risk women) and women with DCIS.

Because high-risk women don’t have cancer yet, it is important to think carefully about whether the possible benefit of tamoxifen in lowering the chance of getting breast cancer is greater than its possible risks.

This Medication Guide reviews the risks and benefits of using tamoxifen to reduce the chance of getting breast cancer in high-risk women and women with DCIS. This guide does not discuss the special benefits and decisions for people who already have breast cancer.

Why do women and men use tamoxifen?

Tamoxifen has more than one use. Tamoxifen is used:

1. to lower the chance of getting breast cancer in women with a higher than normal chance of getting breast cancer in the next 5 years (high-risk women).
2. to lower the chance of getting invasive (spreading) breast cancer in women who had surgery and radiation for ductal carcinoma in situ (DCIS). DCIS means the cancer is only inside the milk ducts.
3. to treat breast cancer in women after they have finished early treatment. Early treatment can include surgery, radiation, and chemotherapy. Tamoxifen may keep the cancer from spreading to other parts of the body. It may also reduce the woman’s chance of getting a new breast cancer.
4. in women and men, to treat breast cancer that has spread to other parts of the body (metastatic breast cancer).

This guide talks only about using tamoxifen to lower the chance of getting breast cancer (#1 and #2 above).

What are the benefits of tamoxifen to lower the chance of getting breast cancer in high-risk women and in women treated for DCIS?

A large U.S. study looked at high-risk women and compared the ones who took tamoxifen for 5 years with others who took a pill without tamoxifen (placebo). High-risk women were defined as women who have a 1.7% or greater chance of getting breast cancer in the next 5 years, based on a special computer program. In this study:

- Out of every 1,000 high-risk women who took a placebo, each year about 7 got breast cancer.
- Out of every 1,000 high-risk women who took tamoxifen, each year about 4 got breast cancer.

The study showed that on average, high-risk women who took tamoxifen lowered their chances of getting breast cancer by 44%, from 7 in 1,000 to 4 in 1,000.

Another U.S. study looked at women with DCIS and compared those who took tamoxifen for 5 years with others who took a placebo. In this study:

- Out of every 1,000 women with DCIS who took placebo, each year about 17 got breast cancer.
- Out of every 1,000 women with DCIS who took tamoxifen, each year about 10 got breast cancer.

The study showed that on average, women with DCIS who took tamoxifen lowered their chances of getting invasive (spreading) breast cancer by 43%, from 17 in 1,000 to 10 in 1,000.

These studies do not mean that taking tamoxifen will lower your personal chance of getting breast cancer. We do not know what the benefits will be for any one woman who takes tamoxifen citrate to reduce her chance of getting breast cancer.

What are the risks of tamoxifen?

In the studies described under “What are the benefits of tamoxifen?”, the high-risk women who took tamoxifen citrate got certain side effects at a higher rate than those who took a placebo. Some of these side effects can cause death.

In one study, in women who still had their uterus:

- Out of every 1,000 women who took a placebo, each year 1 got endometrial cancer (cancer of the lining of the uterus) and none got uterine sarcoma (cancer of the body of the uterus).
- Out of every 1,000 women who took tamoxifen, each year 2 got endometrial cancer and fewer than 1 got uterine sarcoma.

These results show that, on average, in high-risk women who still had their uterus, tamoxifen citrate doubled the chance of getting endometrial cancer from 1 in 1,000 to 2 in 1,000, and it increased the chance of getting uterine sarcoma. This does not mean that taking tamoxifen will double your personal chance of getting endometrial cancer or increase your chance of getting uterine sarcoma. We do not know what this risk will be for any one woman. The risk is different for women who no longer have their uterus.

For all women in this study, taking tamoxifen increased the risk of having a blood clot in their lungs or veins, or of having a stroke. In some cases, women died from these effects.

Tamoxifen increased the risk of getting cataracts (clouding of the lens of the eye) or needing cataract surgery. (See “What are the possible side effects of tamoxifen?” for more details about side effects.)

What don’t we know about taking tamoxifen citrate to reduce the chance of getting breast cancer?

We don’t know:

- if tamoxifen lowers the chance of getting breast cancer in women who have abnormal breast cancer genes (BRCA1 and BRCA2)
- if taking tamoxifen for 5 years reduces the number of breast cancers a woman will get in her lifetime or if it only delays some breast cancers
- if tamoxifen helps a woman live longer
- the effects of taking tamoxifen with hormone replacement therapy (HRT), birth control pills, or androgens (male hormones)
- the benefits of taking tamoxifen if you are less than 35 years old

Studies are being done to learn more about the long-term benefits and risks of using tamoxifen to reduce the chance of getting breast cancer.

What are the possible side effects of tamoxifen?

The most common side effect of tamoxifen is hot flashes. This is not a sign of a serious problem.

The next most common side effect is vaginal discharge. If the discharge is bloody, it could be a sign of a serious problem. [See “Changes in the lining (endometrium) or body of your uterus” below].

Less common but serious side effects of tamoxifen are listed below. These can occur at any time. Call your doctor right away if you have any signs of side effects listed below:

- Changes in the lining (endometrium) or body of your uterus. These changes may mean serious problems are starting, including cancer of the uterus. The signs of changes in the uterus are:
  - Vaginal bleeding or bloody discharge that could be a rusty or brown color. You should call your doctor even if only a small amount of bleeding occurs.
  - Change in your monthly bleeding, such as in the amount or timing of bleeding or increased clotting.
  - Pain or pressure in your pelvis (below your belly button).
- Blood clots in your veins or lungs. These can cause serious problems, including death. You may get clots up to 2 to 3 months after you stop taking tamoxifen citrate. The signs of blood clots are:
  - sudden chest pain, shortness of breath, coughing up blood
  - pain, tenderness, or swelling in one or both of your legs
- Stroke. Stroke can cause serious medical problems, including death. The signs of stroke are:
  - sudden weakness, tingling, or numbness in your face, arm or leg, especially on one side of your body
  - sudden confusion, trouble speaking or understanding
  - sudden trouble seeing in one or both eyes
  - sudden trouble walking, dizziness, loss of balance or coordination
  - sudden severe headache with no known cause
- Cataracts or increased chance of needing cataract surgery. The sign of these problems is slow blurring of your vision.
- Liver problems, including jaundice. The signs of liver problems include lack of appetite and yellowing of your skin or whites of your eyes.

These are not all the possible side effects of tamoxifen. For a complete list, ask your doctor or pharmacist.

Call your doctor for medical advice about side effects. You may report side effects to FDA at 1-800-FDA-1088.

Who should not take tamoxifen?

Do not take tamoxifen for any reason if you

- Are pregnant or plan to become pregnant while taking tamoxifen or during the 2 months after you stop taking tamoxifen. Tamoxifen may harm your unborn baby. It takes about 2 months to clear tamoxifen from your body. To be sure you are not pregnant, you can start taking tamoxifen while you are having your menstrual period. Or, you can take a pregnancy test to be sure you are not pregnant before you begin.
- Are breast feeding. We do not know if tamoxifen can pass through your milk and harm your baby.
- Have had an allergic reaction to tamoxifen or to any of its inactive ingredients.

If you get pregnant while taking tamoxifen, stop taking it right away and contact your doctor. Tamoxifen may harm your unborn baby.

Do not take tamoxifen to lower your chance of getting breast cancer if:

- You ever had a blood clot that needed medical treatment.
- You are taking medicines to thin your blood, like warfarin, (also called Coumadin®).
- Your ability to move around is limited for most of your waking hours.
- You are at risk for blood clots. Your doctor can tell you if you are at high risk for blood clots.
- You do not have a higher than normal chance of getting breast cancer. Your doctor can tell you if you are a high-risk woman.

How should I take tamoxifen?

- Swallow the tablet(s) whole, with water or another non-alcoholic liquid. You can take tamoxifen with or without food. Take your medicine every day. It may be easier to remember if you take it at the same time each day.
- If you forget a dose, take it when you remember, then take the next dose as usual. If it is almost time for your next dose or you remember at your next dose, do not take extra tablets to make up the missed dose.
- Take tamoxifen for 5 years, unless your doctor tells you otherwise.

What should I avoid while taking tamoxifen?

- Do not become pregnant while taking tamoxifen or for 2 months after you stop. Tamoxifen can stop hormonal birth control methods from working. Hormonal methods include birth control pills, patches, injections, rings and implants. Therefore, while taking tamoxifen, use birth control methods that don’t use hormones, such as condoms, diaphragms with spermicide, or plain IUD’s. If you get pregnant, stop taking tamoxifen right away and call your doctor.
- Do not breastfeed. We do not know if tamoxifen can pass through your milk and if it can harm the baby.

What should I do while taking tamoxifen?

- Have regular gynecology check-ups (“female exams”), breast exams and mammograms. Your doctor will tell you how often. These will check for signs of breast cancer and cancer of the endometrium (lining of the uterus). Because tamoxifen does not prevent all breast cancers, and you may get other types of cancers, you need these exams to find any cancers as early as possible.
- Because tamoxifen can cause serious side effects, pay close attention to your body. Signs you should look for are listed in “What are the possible side effects of tamoxifen?”
- Tell all of the doctors that you see that you are taking tamoxifen.
- Tell your doctor right away if you have any new breast lumps.

General information about the safe and effective use of tamoxifen.

Medicines are sometimes prescribed for purposes other than those listed in a Medication Guide. Your doctor has prescribed tamoxifen only for you. Do not give it to other people, even if they have a similar condition, because it may harm them. Do not use it for a condition for which it was not prescribed.

This Medication Guide is a summary of information about tamoxifen for women who use tamoxifen to lower their high chance of getting breast cancer or who have DCIS. If you want more information about tamoxifen, ask your doctor or pharmacist. They can give you information about tamoxifen that is written for health professionals. For more information about tamoxifen or breast cancer, call 1-888-838-2872.

Ingredients: tamoxifen citrate, croscarmellose sodium, lactose monohydrate, magnesium stearate, microcrystalline cellulose, and pregelatinized maize starch.

Brands listed are the trademarks of their respective owners.

This Medication Guide has been approved by the U.S. Food and Drug Administration.

Manufactured For:

Teva Pharmaceuticals

Parsippany, NJ 07054

Rev. B 5/2025

PRINCIPAL DISPLAY PANEL

NDC 0591-2472-60

Tamoxifen Citrate Tablets, USP
10mg
Equivalent to 10 mg tamoxifen

PHARMACIST: Dispense the accompanying Medication Guide to each patient.

60 Tablets Unit-of-use

Rx Only

PRINCIPAL DISPLAY PANEL

NDC 0591-2473-30

Tamoxifen Citrate Tablets, USP
20 mg
Equivalent to 20 mg tamoxifen

PHARMACIST: Dispense the accompanying Medication Guide to each patient.

30 Tablets Unit-of-use

Rx Only